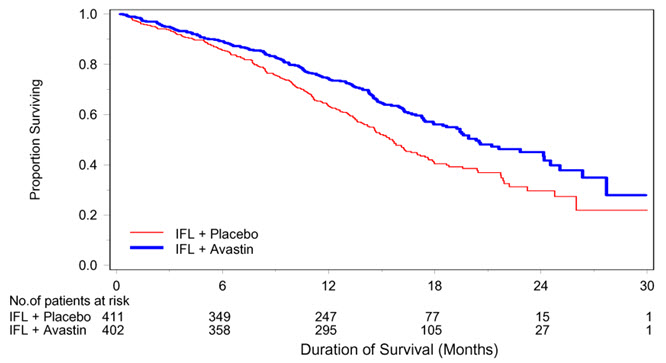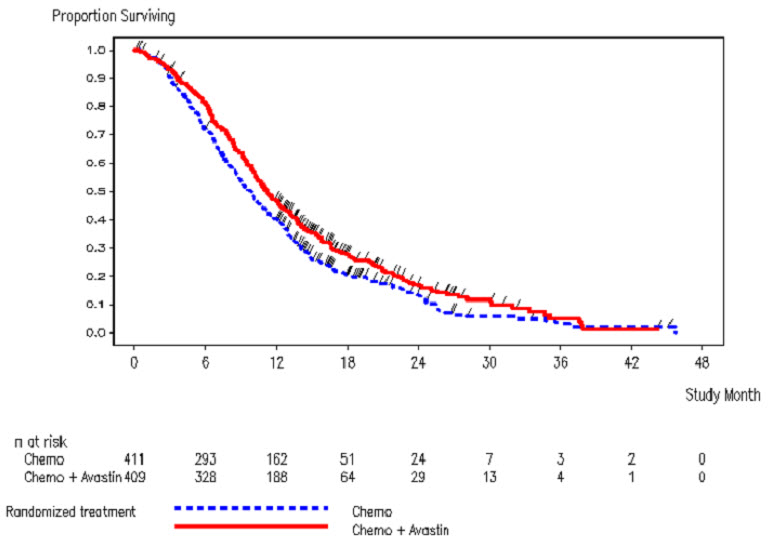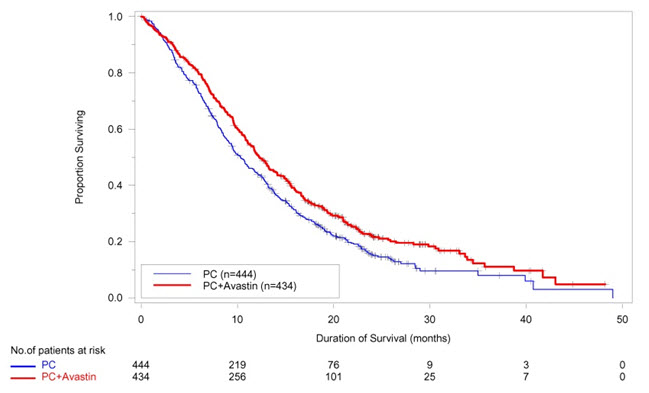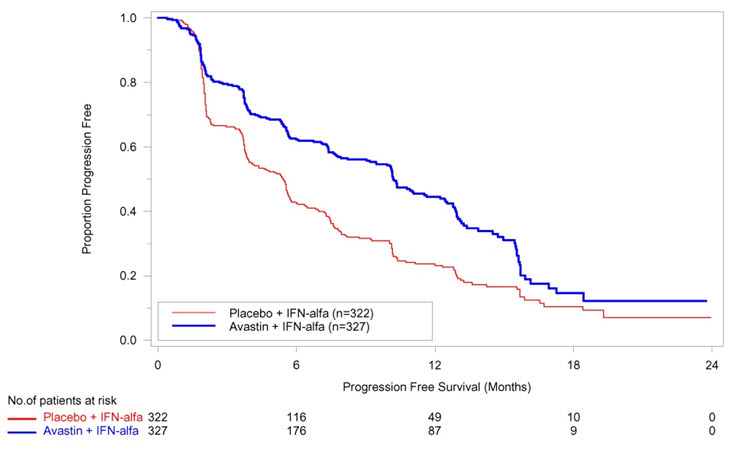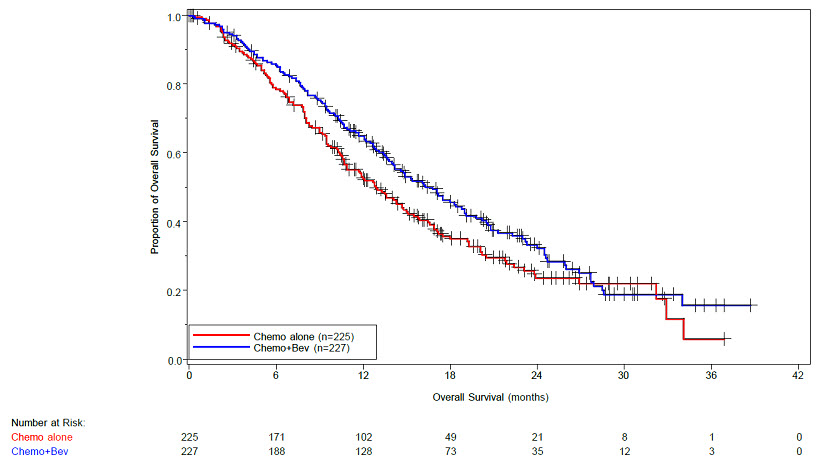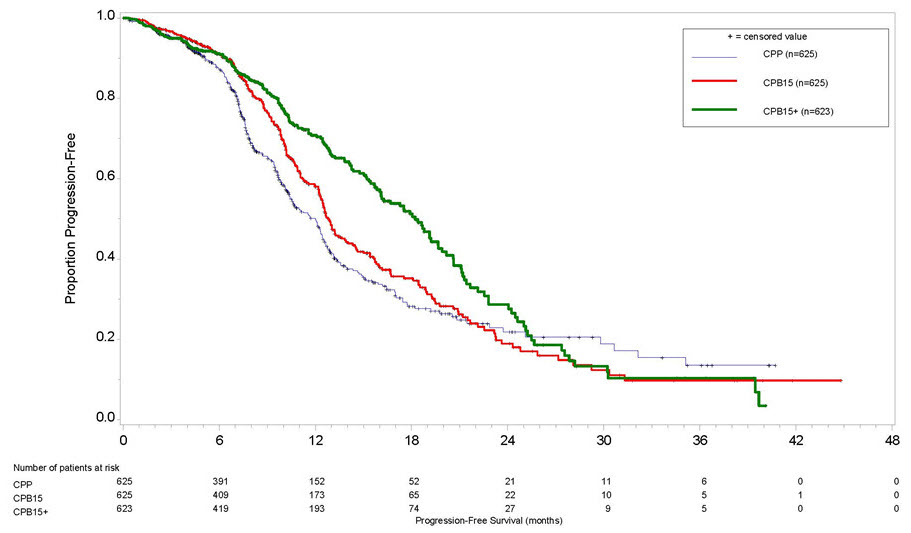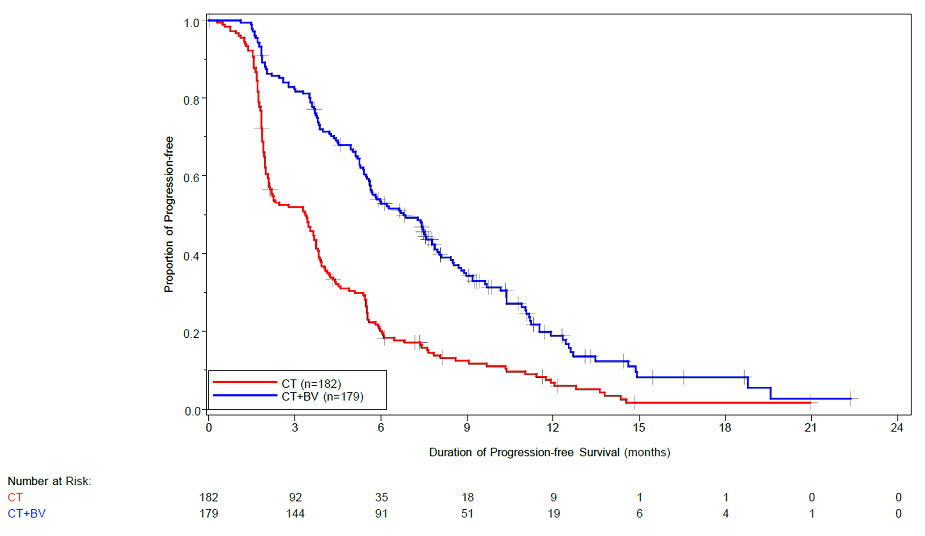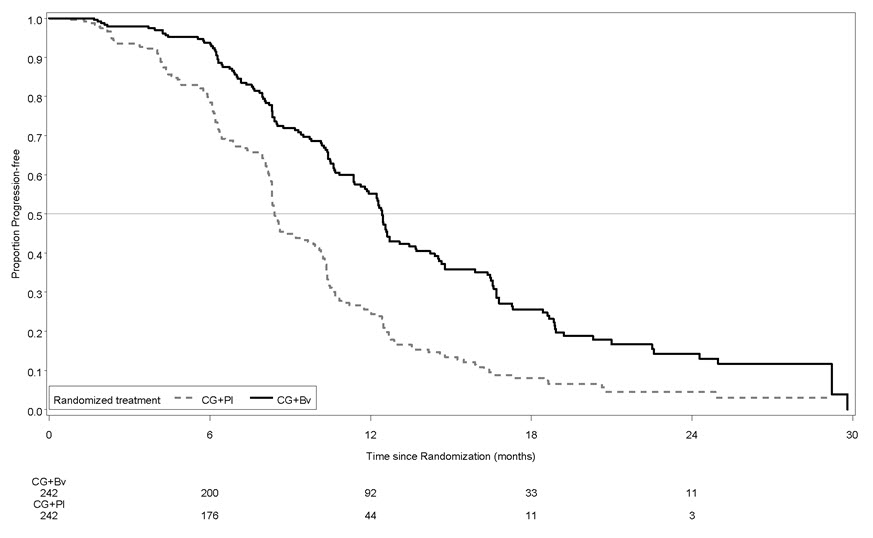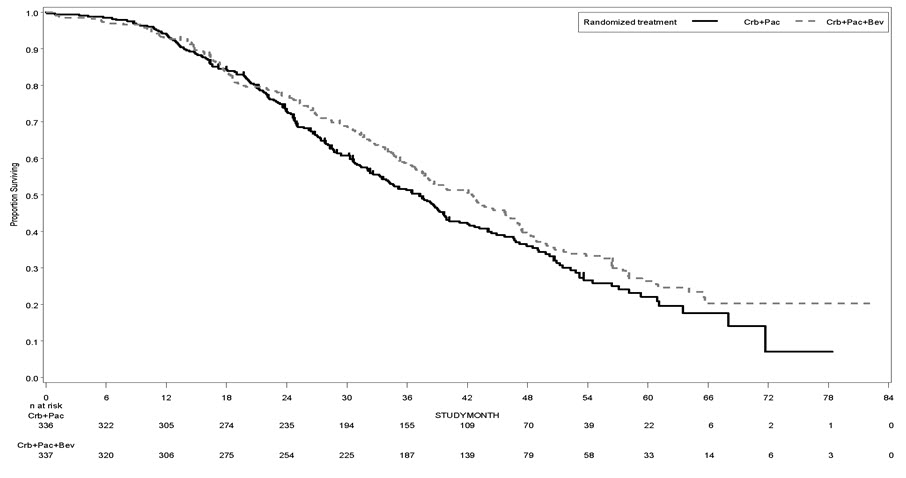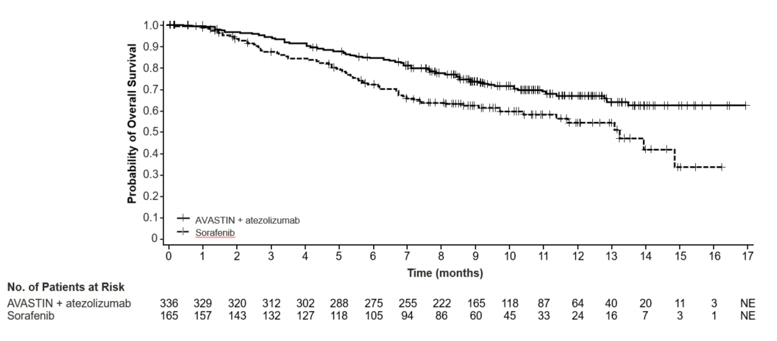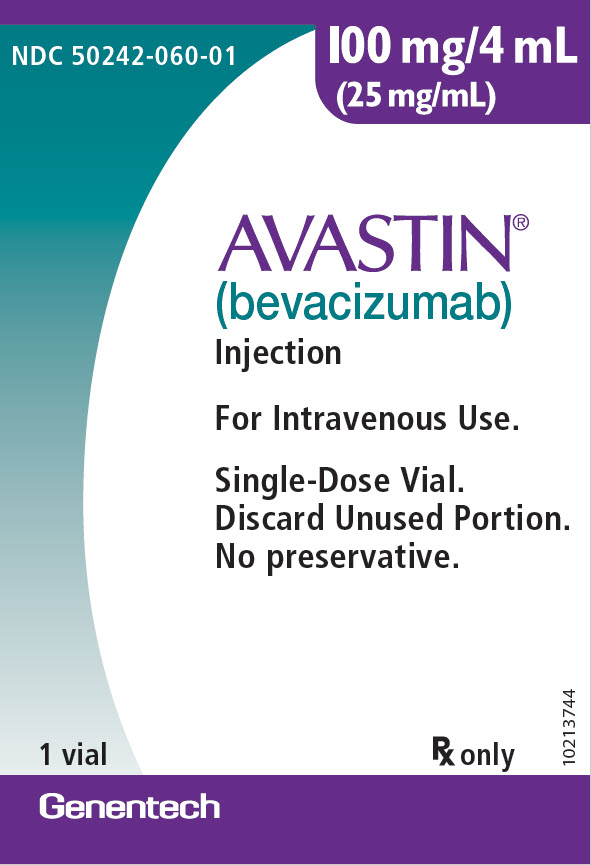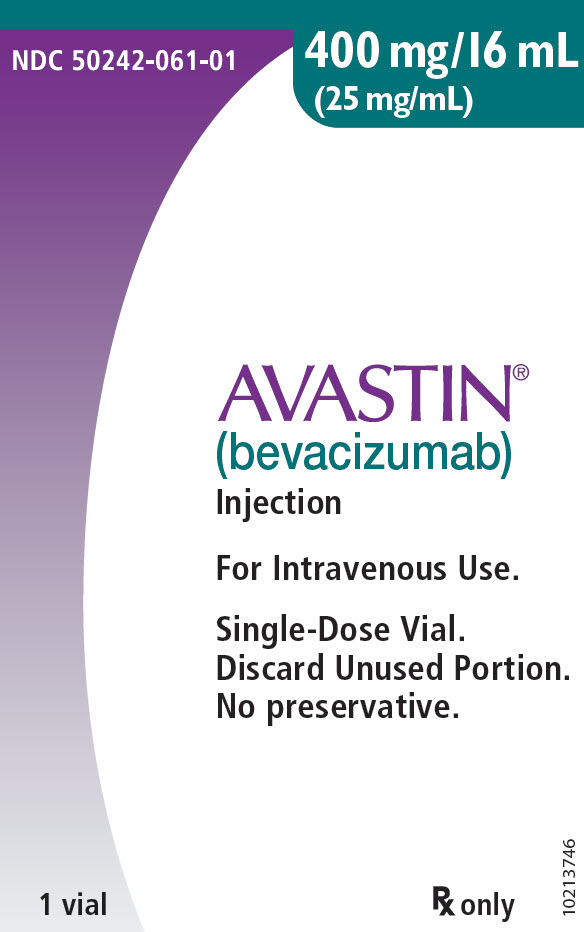 DRUG LABEL: Avastin
NDC: 50242-060 | Form: INJECTION, SOLUTION
Manufacturer: Genentech, Inc.
Category: prescription | Type: HUMAN PRESCRIPTION DRUG LABEL
Date: 20250106

ACTIVE INGREDIENTS: BEVACIZUMAB 100 mg/4 mL
INACTIVE INGREDIENTS: TREHALOSE DIHYDRATE 240 mg/4 mL; SODIUM PHOSPHATE, MONOBASIC, MONOHYDRATE 23.2 mg/4 mL; SODIUM PHOSPHATE, DIBASIC, ANHYDROUS 4.8 mg/4 mL; POLYSORBATE 20 1.6 mg/4 mL; WATER

HIGHLIGHTS OF PRESCRIBING INFORMATION

These highlights do not include all the information needed to use AVASTIN safely and effectively. See full prescribing information for AVASTIN.
AVASTIN® (bevacizumab) injection, for intravenous use
Initial U.S. Approval: 2004

RECENT MAJOR CHANGES

Indications and Usage (1.1) | 9/2022
Dosage and Administration (2.2) | 9/2022
Warnings and Precautions, Infusion-Related Reactions (5.9) | 9/2022

1 INDICATIONS AND USAGE

Avastin is a vascular endothelial growth factor inhibitor indicated for the treatment of:

- Metastatic colorectal cancer, in combination with intravenous fluorouracil-based chemotherapy for first- or second-line treatment. (1.1)
- Metastatic colorectal cancer, in combination with fluoropyrimidine-irinotecan- or fluoropyrimidine-oxaliplatin-based chemotherapy for second-line treatment in patients who have progressed on a first-line bevacizumab product-containing regimen. (1.1)

Limitations of Use: Avastin is not indicated for adjuvant treatment of colon cancer. (1.1)

- Unresectable, locally advanced, recurrent or metastatic non-squamous non-small cell lung cancer, in combination with carboplatin and paclitaxel for first-line treatment. (1.2)
- Recurrent glioblastoma in adults. (1.3)
- Metastatic renal cell carcinoma in combination with interferon alfa. (1.4)
- Persistent, recurrent, or metastatic cervical cancer, in combination with paclitaxel and cisplatin, or paclitaxel and topotecan. (1.5)
- Epithelial ovarian, fallopian tube, or primary peritoneal cancer:
  - in combination with carboplatin and paclitaxel, followed by Avastin as a single agent, for stage III or IV disease following initial surgical resection (1.6)
  - in combination with paclitaxel, pegylated liposomal doxorubicin, or topotecan for platinum-resistant recurrent disease who received no more than 2 prior chemotherapy regimens (1.6)
  - in combination with carboplatin and paclitaxel or carboplatin and gemcitabine, followed by Avastin as a single agent, for platinum-sensitive recurrent disease (1.6)
- Hepatocellular Carcinoma (HCC)
  - in combination with atezolizumab for the treatment of patients with unresectable or metastatic HCC who have not received prior systemic therapy (1.7)

2 DOSAGE AND ADMINISTRATION

Withhold for at least 28 days prior to elective surgery. Do not administer Avastin for 28 days following major surgery and until adequate wound healing. (2.1)

Metastatic colorectal cancer (2.2)

- 5 mg/kg every 2 weeks with bolus-IFL
- 10 mg/kg every 2 weeks with FOLFOX4
- 5 mg/ kg every 2 weeks or 7.5 mg/kg every 3 weeks with fluoropyrimidine-irinotecan- or fluoropyrimidine-oxaliplatin-based chemotherapy after progression on a first-line bevacizumab product-containing regimen

First-line non–squamous non–small cell lung cancer (2.3)

- 15 mg/kg every 3 weeks with carboplatin and paclitaxel

Recurrent glioblastoma (2.4)

- 10 mg/kg every 2 weeks

Metastatic renal cell carcinoma (2.5)

- 10 mg/kg every 2 weeks with interferon alfa

Persistent, recurrent, or metastatic cervical cancer (2.6)

- 15 mg/kg every 3 weeks with paclitaxel and cisplatin, or paclitaxel and topotecan

Stage III or IV epithelial ovarian, fallopian tube or primary peritoneal cancer following initial surgical resection (2.7)

- 15 mg/kg every 3 weeks with carboplatin and paclitaxel for up to 6 cycles, followed by 15 mg/kg every 3 weeks as a single agent, for a total of up to 22 cycles

Platinum-resistant recurrent epithelial ovarian, fallopian tube or primary peritoneal cancer (2.7)

- 10 mg/kg every 2 weeks with paclitaxel, pegylated liposomal doxorubicin, or topotecan given every week
- 15 mg/kg every 3 weeks with topotecan given every 3 weeks

Platinum-sensitive recurrent epithelial ovarian, fallopian tube, or primary peritoneal cancer (2.7)

- 15 mg/kg every 3 weeks with carboplatin and paclitaxel for 6-8 cycles, followed by 15 mg/kg every 3 weeks as a single agent
- 15 mg/kg every 3 weeks with carboplatin and gemcitabine for 6-10 cycles, followed by 15 mg/kg every 3 weeks as a single agent

Hepatocellular Carcinoma (2.8)

- 15 mg/kg after administration of 1,200 mg of atezolizumab every 3 weeks

Administer as an intravenous infusion after dilution. See full Prescribing Information for preparation and administration instructions and dosage modifications for adverse reactions (2.9, 2.10)

3 DOSAGE FORMS AND STRENGTHS

Injection: 100 mg/4 mL (25 mg/mL) or 400 mg/16 mL (25 mg/mL) in a single-dose vial (3)

4 CONTRAINDICATIONS

None (4)

5 WARNINGS AND PRECAUTIONS

- Gastrointestinal Perforations and Fistula: Discontinue for gastrointestinal perforations, tracheoesophageal fistula, grade 4 fistula, or fistula formation involving any organ (5.1)
- Surgery and Wound Healing Complications: In patients who experience wound healing complications during Avastin treatment, withhold Avastin until adequate wound healing. Withhold for at least 28 days prior to elective surgery. Do not administer Avastin for at least 28 days following a major surgery, and until adequate wound healing. The safety of resumption of AVASTIN after resolution of wound healing complication has not been established. Discontinue for wound healing complication of necrotizing fasciitis. (5.2)
- Hemorrhage: Severe or fatal hemorrhages have occurred. Do not administer for recent hemoptysis. Discontinue for Grade 3-4 hemorrhage (5.3)
- Arterial Thromboembolic Events (ATE): Discontinue for severe ATE. (5.4)
- Venous Thromboembolic Events (VTE): Discontinue for Grade 4 VTE. (5.5)
- Hypertension: Monitor blood pressure and treat hypertension. Withhold if not medically controlled; resume once controlled. Discontinue for hypertensive crisis or hypertensive encephalopathy. (5.6)
- Posterior Reversible Encephalopathy Syndrome (PRES): Discontinue. (5.7)
- Renal Injury and Proteinuria: Monitor urine protein. Discontinue for nephrotic syndrome. Withhold until less than 2 grams of protein in urine. (5.8)
- Infusion-Related Reactions: Decrease rate for infusion-related reactions. Discontinue for severe infusion-related reactions and administer medical therapy. (5.9)
- Embryo-Fetal Toxicity: May cause fetal harm. Advise females of potential risk to fetus and need for use of effective contraception. (5.10, 8.1, 8.3)
- Ovarian Failure: Advise females of the potential risk. (5.11, 8.3)
- Congestive Heart Failure (CHF): Discontinue Avastin in patients who develop CHF. (5.12)

6 ADVERSE REACTIONS

Most common adverse reactions incidence (incidence > 10%) are epistaxis, headache, hypertension, rhinitis, proteinuria, taste alteration, dry skin, hemorrhage, lacrimation disorder, back pain and exfoliative dermatitis. (6.1)

To report SUSPECTED ADVERSE REACTIONS, contact Genentech, Inc. at 1-888-835-2555 or FDA at 1-800-FDA-1088 or www.fda.gov/medwatch.

8 USE IN SPECIFIC POPULATIONS

Lactation: Advise not to breastfeed. (8.2)

FULL PRESCRIBING INFORMATION

1 INDICATIONS AND USAGE

1.1 Metastatic Colorectal Cancer

Avastin, in combination with intravenous fluorouracil-based chemotherapy, is indicated for the first-or second-line treatment of patients with metastatic colorectal cancer (mCRC).

Avastin, in combination with fluoropyrimidine-irinotecan- or fluoropyrimidine-oxaliplatin-based chemotherapy, is indicated for the second-line treatment of patients with mCRC who have progressed on a first-line bevacizumab product-containing regimen.

Limitations of Use: Avastin is not indicated for adjuvant treatment of colon cancer [see Clinical Studies (14.2)].

1.2 First-Line Non-Squamous Non–Small Cell Lung Cancer

Avastin, in combination with carboplatin and paclitaxel, is indicated for the first-line treatment of patients with unresectable, locally advanced, recurrent or metastatic non–squamous non–small cell lung cancer (NSCLC).

1.3 Recurrent Glioblastoma

Avastin is indicated for the treatment of recurrent glioblastoma (GBM) in adults.

1.4 Metastatic Renal Cell Carcinoma

Avastin, in combination with interferon alfa, is indicated for the treatment of metastatic renal cell carcinoma (mRCC).

1.5 Persistent, Recurrent, or Metastatic Cervical Cancer

Avastin, in combination with paclitaxel and cisplatin or paclitaxel and topotecan, is indicated for the treatment of patients with persistent, recurrent, or metastatic cervical cancer.

1.6 Epithelial Ovarian, Fallopian Tube, or Primary Peritoneal Cancer

Avastin, in combination with carboplatin and paclitaxel, followed by Avastin as a single agent, is indicated for the treatment of patients with stage III or IV epithelial ovarian, fallopian tube, or primary peritoneal cancer following initial surgical resection.

Avastin, in combination with paclitaxel, pegylated liposomal doxorubicin, or topotecan, is indicated for the treatment of patients with platinum-resistant recurrent epithelial ovarian, fallopian tube or primary peritoneal cancer who received no more than 2 prior chemotherapy regimens.

Avastin, in combination with carboplatin and paclitaxel, or with carboplatin and gemcitabine, followed by Avastin as a single agent, is indicated for the treatment of patients with platinum-sensitive recurrent epithelial ovarian, fallopian tube, or primary peritoneal cancer.

1.7 Hepatocellular Carcinoma

Avastin, in combination with atezolizumab, is indicated for the treatment of patients with unresectable or metastatic hepatocellular carcinoma (HCC) who have not received prior systemic therapy.

2 DOSAGE AND ADMINISTRATION

2.1 Important Administration Information

Withhold for at least 28 days prior to elective surgery. Do not administer Avastin until at least 28 days following major surgery and until adequate wound healing.

2.2 Metastatic Colorectal Cancer

The recommended dosage when Avastin is administered in combination with intravenous fluorouracil-based chemotherapy is:

- 5 mg/kg intravenously every 2 weeks in combination with bolus-IFL.
- 10 mg/kg intravenously every 2 weeks in combination with FOLFOX4.
- 5 mg/kg intravenously every 2 weeks or 7.5 mg/kg intravenously every 3 weeks in combination with fluoropyrimidine-irinotecan- or fluoropyrimidine-oxaliplatin-based chemotherapy in patients who have progressed on a first-line bevacizumab product-containing regimen.

2.3 First-Line Non-Squamous Non-Small Cell Lung Cancer

The recommended dosage is 15 mg/kg intravenously every 3 weeks in combination with carboplatin and paclitaxel.

2.4 Recurrent Glioblastoma

The recommended dosage is 10 mg/kg intravenously every 2 weeks.

2.5 Metastatic Renal Cell Carcinoma

The recommended dosage is 10 mg/kg intravenously every 2 weeks in combination with interferon alfa.

2.6 Persistent, Recurrent, or Metastatic Cervical Cancer

The recommended dosage is 15 mg/kg intravenously every 3 weeks in combination with paclitaxel and cisplatin or in combination with paclitaxel and topotecan.

2.7 Epithelial Ovarian, Fallopian Tube or Primary Peritoneal Cancer

Stage III or IV Disease Following Initial Surgical Resection

The recommended dosage is 15 mg/kg intravenously every 3 weeks in combination with carboplatin and paclitaxel for up to 6 cycles, followed by Avastin 15 mg/kg every 3 weeks as a single agent for a total of up to 22 cycles or until disease progression, whichever occurs earlier.

Recurrent Disease

Platinum Resistant

The recommended dosage is 10 mg/kg intravenously every 2 weeks in combination with paclitaxel, pegylated liposomal doxorubicin, or topotecan (every week).

The recommended dosage is 15 mg/kg intravenously every 3 weeks in combination with topotecan (every 3 weeks).

Platinum Sensitive

The recommended dosage is 15 mg/kg intravenously every 3 weeks, in combination with carboplatin and paclitaxel for 6 to 8 cycles, followed by Avastin 15 mg/kg every 3 weeks as a single agent until disease progression.

The recommended dosage is 15 mg/kg intravenously every 3 weeks, in combination with carboplatin and gemcitabine for 6 to 10 cycles, followed by Avastin 15 mg/kg every 3 weeks as a single agent until disease progression.

2.8 Hepatocellular Carcinoma

The recommended dosage is 15 mg/kg intravenously after administration of 1,200 mg of atezolizumab intravenously on the same day, every 3 weeks until disease progression or unacceptable toxicity.

Refer to the Prescribing Information for atezolizumab prior to initiation for recommended dosage information.

2.9 Dosage Modifications for Adverse Reactions

Table 1 describes dosage modifications for specific adverse reactions. No dose reductions for Avastin are recommended.

Table 1: Dosage Modifications for Adverse Reactions
Adverse Reaction | Severity | Dosage Modification
Gastrointestinal Perforations and Fistulae [see Warnings and Precautions (5.1)]. | - Gastrointestinal perforation, any grade - Tracheoesophageal fistula, any grade - Fistula, Grade 4 - Fistula formation involving any internal organ | Discontinue Avastin
Wound Healing Complications [see Warnings and Precautions (5.2)]. | - Any | Withhold AVASTIN until adequate wound healing.The safety of resumption of AVASTIN after resolution of wound healing complications has not been established.
Wound Healing Complications [see Warnings and Precautions (5.2)]. | - Necrotizing fasciitis | Discontinue Avastin
Hemorrhage [see Warnings and Precautions (5.3)]. | - Grade 3 or 4 | Discontinue Avastin
Hemorrhage [see Warnings and Precautions (5.3)]. | - Recent history of hemoptysis of 1/2 teaspoon (2.5 mL) or more | Withhold Avastin
Thromboembolic Events [see Warnings and Precautions (5.4, 5.5)]. | - Arterial thromboembolism, severe | Discontinue Avastin
Thromboembolic Events [see Warnings and Precautions (5.4, 5.5)]. | - Venous thromboembolism, Grade 4 | Discontinue Avastin
Hypertension [see Warnings and Precautions (5.6)]. | - Hypertensive crisis - Hypertensive encephalopathy | Discontinue Avastin
Hypertension [see Warnings and Precautions (5.6)]. | - Hypertension, severe | Withhold Avastin if not controlled with medical management; resume once controlled
Posterior Reversible Encephalopathy Syndrome (PRES) [see Warnings and Precautions (5.7)]. | - Any | Discontinue Avastin
Renal Injury and Proteinuria [see Warnings and Precautions (5.8)]. | - Nephrotic syndrome | Discontinue Avastin
Renal Injury and Proteinuria [see Warnings and Precautions (5.8)]. | - Proteinuria greater than or equal to 2 grams per 24 hours in absence of nephrotic syndrome | Withhold Avastin until proteinuria less than 2 grams per 24 hours
Infusion-Related Reactions [see Warnings and Precautions (5.9)]. | - Severe | Discontinue Avastin
Infusion-Related Reactions [see Warnings and Precautions (5.9)]. | - Clinically significant | Interrupt infusion; resume at a decreased rate of infusion after symptoms resolve
Infusion-Related Reactions [see Warnings and Precautions (5.9)]. | - Mild, clinically insignificant | Decrease infusion rate
Congestive Heart Failure [see Warnings and Precautions (5.12)]. | Any | Discontinue Avastin

2.10 Preparation and Administration

Preparation

- Use appropriate aseptic technique.
- Use sterile needle and syringe to prepare Avastin.
- Visually inspect vial for particulate matter and discoloration prior to preparation for administration. Discard vial if solution is cloudy, discolored or contains particulate matter.
- Withdraw necessary amount of Avastin and dilute in a total volume of 100 mL of 0.9% Sodium Chloride Injection, USP. DO NOT ADMINISTER OR MIX WITH DEXTROSE SOLUTION.
- Discard any unused portion left in a vial, as the product contains no preservatives.
- Diluted Avastin solution may be stored at 2°C to 8°C (36°F to 46°F) for up to 8 hours, if not used immediately.
- No incompatibilities between Avastin and polyvinylchloride or polyolefin bags have been observed.

Administration

- Administer as an intravenous infusion.
- First infusion: Administer infusion over 90 minutes.
- Subsequent infusions: Administer second infusion over 60 minutes if first infusion is tolerated. Administer all subsequent infusions over 30 minutes if second infusion over 60 minutes is tolerated.

3 DOSAGE FORMS AND STRENGTHS

Injection: 100 mg/4 mL (25 mg/mL) or 400 mg/16 mL (25 mg/mL) clear to slightly opalescent, colorless to pale brown solution in a single-dose vial.

4 CONTRAINDICATIONS

None.

5 WARNINGS AND PRECAUTIONS

5.1 Gastrointestinal Perforations and Fistulae

Serious, and sometimes fatal, gastrointestinal perforation occurred at a higher incidence in patients receiving Avastin compared to patients receiving chemotherapy. The incidence ranged from 0.3% to 3% across clinical studies, with the highest incidence in patients with a history of prior pelvic radiation. Perforation can be complicated by intra-abdominal abscess, fistula formation, and the need for diverting ostomies. The majority of perforations occurred within 50 days of the first dose [see Adverse Reactions (6.1)].

Serious fistulae (including, tracheoesophageal, bronchopleural, biliary, vaginal, renal and bladder sites) occurred at a higher incidence in patients receiving Avastin compared to patients receiving chemotherapy. The incidence ranged from < 1% to 1.8% across clinical studies, with the highest incidence in patients with cervical cancer. The majority of fistulae occurred within 6 months of the first dose. Patients who develop a gastrointestinal vaginal fistula may also have a bowel obstruction and require surgical intervention, as well as a diverting ostomy.

Avoid Avastin in patients with ovarian cancer who have evidence of recto-sigmoid involvement by pelvic examination or bowel involvement on CT scan or clinical symptoms of bowel obstruction. Discontinue in patients who develop gastrointestinal perforation, tracheoesophageal fistula or any Grade 4 fistula. Discontinue in patients with fistula formation involving any internal organ.

5.2 Surgery and Wound Healing Complications

In a controlled clinical study in which Avastin was not administered within 28 days of major surgical procedures, the incidence of wound healing complications, including serious and fatal complications, was 15% in patients with mCRC who underwent surgery while receiving Avastin and 4% in patients who did not receive Avastin. In a controlled clinical study in patients with relapsed or recurrent GBM, the incidence of wound healing events was 5% in patients who received Avastin and 0.7% in patients who did not receive Avastin [see Adverse Reactions (6.1)].

In patients who experience wound healing complications during Avastin treatment, withhold Avastin until adequate wound healing. Withhold for at least 28 days prior to elective surgery. Do not administer for at least 28 days following major surgery and until adequate wound healing. The safety of resumption of AVASTIN after resolution of wound healing complications has not been established [see Dosage and Administration (2.9)].

Necrotizing fasciitis including fatal cases, has been reported in patients receiving Avastin, usually secondary to wound healing complications, gastrointestinal perforation or fistula formation. Discontinue Avastin in patients who develop necrotizing fasciitis.

5.3 Hemorrhage

Avastin can result in two distinct patterns of bleeding: minor hemorrhage, which is most commonly Grade 1 epistaxis, and serious hemorrhage, which in some cases has been fatal. Severe or fatal hemorrhage, including hemoptysis, gastrointestinal bleeding, hematemesis, CNS hemorrhage, epistaxis, and vaginal bleeding, occurred up to 5-fold more frequently in patients receiving Avastin compared to patients receiving chemotherapy alone. Across clinical studies, the incidence of Grades 3-5 hemorrhagic events ranged from 0.4% to 7% in patients receiving Avastin [see Adverse Reactions (6.1)].

Serious or fatal pulmonary hemorrhage occurred in 31% of patients with squamous NSCLC and 4% of patients with non-squamous NSCLC receiving Avastin with chemotherapy compared to none of the patients receiving chemotherapy alone.

An evaluation for the presence of varices is recommended within 6 months of initiation of Avastin in patients with HCC. There is lack of clinical data to support the safety of Avastin in patients with variceal bleeding within 6 months prior to treatment, untreated or incompletely treated varices with bleeding, or high risk of bleeding because these patients were excluded from clinical trials of Avastin in HCC [see Clinical Studies (14.10)].

Do not administer Avastin to patients with recent history of hemoptysis of 1/2 teaspoon or more of red blood. Discontinue in patients who develop a Grades 3-4 hemorrhage.

5.4 Arterial Thromboembolic Events

Serious, sometimes fatal, arterial thromboembolic events (ATE) including cerebral infarction, transient ischemic attacks, myocardial infarction, and angina, occurred at a higher incidence in patients receiving Avastin compared to patients receiving chemotherapy. Across clinical studies, the incidence of Grades 3-5 ATE was 5% in patients receiving Avastin with chemotherapy compared to ≤2% in patients receiving chemotherapy alone; the highest incidence occurred in patients with GBM. The risk of developing ATE was increased in patients with a history of arterial thromboembolism, diabetes, or >65 years [see Use in Specific Populations (8.5)].

Discontinue in patients who develop a severe ATE. The safety of reinitiating Avastin after an ATE is resolved is not known.

5.5 Venous Thromboembolic Events

An increased risk of venous thromboembolic events (VTE) was observed across clinical studies [see Adverse Reactions (6.1)]. In Study GOG-0240, Grades 3-4 VTE occurred in 11% of patients receiving Avastin with chemotherapy compared with 5% of patients receiving chemotherapy alone. In EORTC 26101, the incidence of Grades 3-4 VTE was 5% in patients receiving Avastin with chemotherapy compared to 2% in patients receiving chemotherapy alone.

Discontinue Avastin in patients with a Grade 4 VTE, including pulmonary embolism.

5.6 Hypertension

Severe hypertension occurred at a higher incidence in patients receiving Avastin as compared to patients receiving chemotherapy alone. Across clinical studies, the incidence of Grades 3-4 hypertension ranged from 5% to 18%.

Monitor blood pressure every two to three weeks during treatment with Avastin. Treat with appropriate anti-hypertensive therapy and monitor blood pressure regularly. Continue to monitor blood pressure at regular intervals in patients with Avastin-induced or -exacerbated hypertension after discontinuing Avastin. Withhold Avastin in patients with severe hypertension that is not controlled with medical management; resume once controlled with medical management. Discontinue in patients who develop hypertensive crisis or hypertensive encephalopathy.

5.7 Posterior Reversible Encephalopathy Syndrome

Posterior reversible encephalopathy syndrome (PRES) was reported in < 0.5% of patients across clinical studies. The onset of symptoms occurred from 16 hours to 1 year after the first dose. PRES is a neurological disorder which can present with headache, seizure, lethargy, confusion, blindness and other visual and neurologic disturbances. Mild to severe hypertension may be present. Magnetic resonance imaging is necessary to confirm the diagnosis of PRES.

Discontinue Avastin in patients who develop PRES. Symptoms usually resolve or improve within days after discontinuing Avastin, although some patients have experienced ongoing neurologic sequelae. The safety of reinitiating Avastin in patients who developed PRES is not known.

5.8 Renal Injury and Proteinuria

The incidence and severity of proteinuria was higher in patients receiving Avastin as compared to patients receiving chemotherapy. Grade 3 (defined as urine dipstick 4+ or > 3.5 grams of protein per 24 hours) to Grade 4 (defined as nephrotic syndrome) ranged from 0.7% to 7% in clinical studies. The overall incidence of proteinuria (all grades) was only adequately assessed in Study BO17705, in which the incidence was 20%. Median onset of proteinuria was 5.6 months (15 days to 37 months) after initiating Avastin. Median time to resolution was 6.1 months (95% CI: 2.8, 11.3). Proteinuria did not resolve in 40% of patients after median follow-up of 11.2 months and required discontinuation of Avastin in 30% of the patients who developed proteinuria [see Adverse Reactions (6.1)].

In an exploratory, pooled analysis of patients from seven randomized clinical studies, 5% of patients receiving Avastin with chemotherapy experienced Grades 2-4 (defined as urine dipstick 2+ or greater or > 1 gram of protein per 24 hours or nephrotic syndrome) proteinuria. Grades 2-4 proteinuria resolved in 74% of patients. Avastin was reinitiated in 42% of patients. Of the 113 patients who reinitiated Avastin, 48% experienced a second episode of Grades 2-4 proteinuria.

Nephrotic syndrome occurred in < 1% of patients receiving Avastin across clinical studies, in some instances with fatal outcome. In a published case series, kidney biopsy of 6 patients with proteinuria showed findings consistent with thrombotic microangiopathy. Results of a retrospective analysis of 5805 patients who received Avastin with chemotherapy and 3713 patients who received chemotherapy alone, showed higher rates of elevated serum creatinine levels (between 1.5 to 1.9 times baseline levels) in patients who received Avastin. Serum creatinine levels did not return to baseline in approximately one-third of patients who received Avastin.

Monitor proteinuria by dipstick urine analysis for the development or worsening of proteinuria with serial urinalyses during Avastin therapy. Patients with a 2+ or greater urine dipstick reading should undergo further assessment with a 24-hour urine collection. Withhold for proteinuria greater than or equal to 2 grams per 24 hours and resume when less than 2 grams per 24 hours. Discontinue in patients who develop nephrotic syndrome.

Data from a postmarketing safety study showed poor correlation between UPCR (Urine Protein/Creatinine Ratio) and 24-hour urine protein [Pearson Correlation 0.39 (95% CI: 0.17, 0.57)].

5.9 Infusion-Related Reactions

Infusion-related reactions reported across clinical studies and postmarketing experience include hypertension, hypertensive crises associated with neurologic signs and symptoms, wheezing, oxygen desaturation, Grade 3 hypersensitivity, anaphylactoid/anaphylactic reactions, chest pain, headaches, rigors, and diaphoresis. In clinical studies, infusion-related reactions with the first dose occurred in < 3% of patients and severe reactions occurred in 0.4% of patients.

Decrease the rate of infusion for mild, clinically insignificant infusion-related reactions. Interrupt the infusion in patients with clinically significant infusion-related reactions and consider resuming at a slower rate following resolution. Discontinue in patients who develop a severe infusion-related reaction and administer appropriate medical therapy (e.g., epinephrine, corticosteroids, intravenous antihistamines, bronchodilators and/or oxygen).

5.10 Embryo-Fetal Toxicity

Based on its mechanism of action and findings from animal studies, Avastin may cause fetal harm when administered to pregnant women. Congenital malformations were observed with the administration of bevacizumab to pregnant rabbits during organogenesis every 3 days at a dose as low as a clinical dose of 10 mg/kg. Furthermore, animal models link angiogenesis and VEGF and VEGFR2 to critical aspects of female reproduction, embryo-fetal development, and postnatal development. Advise pregnant women of the potential risk to a fetus. Advise females of reproductive potential to use effective contraception during treatment with Avastin and for 6 months after the last dose [see Use in Specific Populations (8.1, 8.3)].

5.11 Ovarian Failure

The incidence of ovarian failure was 34% vs. 2% in premenopausal women receiving Avastin with chemotherapy as compared to those receiving chemotherapy alone for adjuvant treatment of a solid tumor. After discontinuing Avastin, recovery of ovarian function at all time points during the post-treatment period was demonstrated in 22% of women receiving Avastin. Recovery of ovarian function is defined as resumption of menses, a positive serum β-HCG pregnancy test, or an FSH level < 30 mIU/mL during the post-treatment period. Long-term effects of Avastin on fertility are unknown. Inform females of reproductive potential of the risk of ovarian failure prior to initiating Avastin [see Adverse Reactions (6.1), Use in Specific Populations (8.3)].

5.12 Congestive Heart Failure (CHF)

Avastin is not indicated for use with anthracycline-based chemotherapy. The incidence of Grade ≥ 3 left ventricular dysfunction was 1% in patients receiving Avastin compared to 0.6% of patients receiving chemotherapy alone. Among patients who received prior anthracycline treatment, the rate of CHF was 4% for patients receiving Avastin with chemotherapy as compared to 0.6% for patients receiving chemotherapy alone.

In previously untreated patients with a hematological malignancy, the incidence of CHF and decline in left ventricular ejection fraction (LVEF) were increased in patients receiving Avastin with anthracycline-based chemotherapy compared to patients receiving placebo with the same chemotherapy regimen. The proportion of patients with a decline in LVEF from baseline of ≥ 20% or a decline from baseline of 10% to < 50%, was 10% in patients receiving Avastin with chemotherapy compared to 5% in patients receiving chemotherapy alone. Time to onset of left-ventricular dysfunction or CHF was 1 to 6 months after the first dose in at least 85% of the patients and was resolved in 62% of the patients who developed CHF in the Avastin arm compared to 82% in the placebo arm. Discontinue Avastin in patients who develop CHF.

6 ADVERSE REACTIONS

The following clinically significant adverse reactions are described elsewhere in the labeling:

- Gastrointestinal Perforations and Fistulae [see Warnings and Precautions (5.1)].
- Surgery and Wound Healing Complications [see Warnings and Precautions (5.2)].
- Hemorrhage [see Warnings and Precautions (5.3)].
- Arterial Thromboembolic Events [see Warnings and Precautions (5.4)].
- Venous Thromboembolic Events [see Warnings and Precautions (5.5)].
- Hypertension [see Warnings and Precautions (5.6)].
- Posterior Reversible Encephalopathy Syndrome [see Warnings and Precautions (5.7)].
- Renal Injury and Proteinuria [see Warnings and Precautions (5.8)].
- Infusion-Related Reactions [see Warnings and Precautions (5.9)].
- Ovarian Failure [see Warnings and Precautions (5.11)].
- Congestive Heart Failure [see Warnings and Precautions (5.12)].

6.1 Clinical Trials Experience

Because clinical studies are conducted under widely varying conditions, adverse reaction rates observed in the clinical studies of a drug cannot be directly compared to rates in the clinical studies of another drug and may not reflect the rates observed in practice.

The safety data in Warnings and Precautions and described below reflect exposure to Avastin in 4463 patients including those with mCRC (AVF2107g, E3200), non-squamous NSCLC (E4599), GBM (EORTC 26101), mRCC (BO17705), cervical cancer (GOG-0240), epithelial ovarian, fallopian tube, or primary peritoneal cancer (MO22224, AVF4095, GOG-0213, and GOG-0218), or HCC (IMbrave150) at the recommended dose and schedule for a median of 6 to 23 doses. The most common adverse reactions observed in patients receiving Avastin as a single agent or in combination with other anti-cancer therapies at a rate > 10% were epistaxis, headache, hypertension, rhinitis, proteinuria, taste alteration, dry skin, hemorrhage, lacrimation disorder, back pain, and exfoliative dermatitis.

Across clinical studies, Avastin was discontinued in 8% to 22% of patients because of adverse reactions [see Clinical Studies (14)].

Metastatic Colorectal Cancer

In Combination with bolus-IFL

The safety of Avastin was evaluated in 392 patients who received at least one dose of Avastin in a double-blind, active-controlled study (AVF2107g), which compared Avastin (5 mg/kg every 2 weeks) with bolus-IFL to placebo with bolus-IFL in patients with mCRC [see Clinical Studies (14.1)]. Patients were randomized (1:1:1) to placebo with bolus-IFL, Avastin with bolus-IFL, or Avastin with fluorouracil and leucovorin. The demographics of the safety population were similar to the demographics of the efficacy population. All Grades 3–4 adverse reactions and selected Grades 1–2 adverse reactions (i.e., hypertension, proteinuria, thromboembolic events) were collected in the entire study population. Adverse reactions are presented in Table 2.

Table 2: Grades 3-4 Adverse Reactions Occurring at Higher Incidence (≥2%) in Patients Receiving Avastin vs. Placebo in Study AVF2107g
Adverse Reaction [NCI-CTC version 3] | Avastin with IFL (N=392) | Placebo with IFL (N=396)
Hematology
Leukopenia | 37% | 31%
Neutropenia | 21% | 14%
Gastrointestinal
Diarrhea | 34% | 25%
Abdominal pain | 8% | 5%
Constipation | 4% | 2%
Vascular
Hypertension | 12% | 2%
Deep vein thrombosis | 9% | 5%
Intra-abdominal thrombosis | 3% | 1%
Syncope | 3% | 1%
General
Asthenia | 10% | 7%
Pain | 8% | 5%

In Combination with FOLFOX4

The safety of Avastin was evaluated in 521 patients in an open-label, active-controlled study (E3200) in patients who were previously treated with irinotecan and fluorouracil for initial therapy for mCRC. Patients were randomized (1:1:1) to FOLFOX4, Avastin (10 mg/kg every 2 weeks prior to FOLFOX4 on Day 1) with FOLFOX4, or Avastin alone (10 mg/kg every 2 weeks). Avastin was continued until disease progression or unacceptable toxicity.

The demographics of the safety population were similar to the demographics of the efficacy population.

Selected Grades 3–5 non-hematologic and Grades 4–5 hematologic occurring at a higher incidence (≥ 2%) in patients receiving Avastin with FOLFOX4 compared to FOLFOX4 alone were fatigue (19% vs. 13%), diarrhea (18% vs. 13%), sensory neuropathy (17% vs. 9%), nausea (12% vs. 5%), vomiting (11% vs. 4%), dehydration (10% vs. 5%), hypertension (9% vs. 2%), abdominal pain (8% vs. 5%), hemorrhage (5% vs. 1%), other neurological (5% vs. 3%), ileus (4% vs. 1%) and headache (3% vs. 0%). These data are likely to under-estimate the true adverse reaction rates due to the reporting mechanisms.

First-Line Non Squamous Non-Small Cell Lung Cancer

The safety of Avastin was evaluated as first-line treatment in 422 patients with unresectable NSCLC who received at least one dose of Avastin in an active-controlled, open-label, multicenter trial (E4599) [see Clinical Studies (14.3)]. Chemotherapy naïve patients with locally advanced, metastatic or recurrent non–squamous NSCLC were randomized (1:1) to receive six 21-day cycles of paclitaxel and carboplatin with or without Avastin (15 mg/kg every 3 weeks). After completion or upon discontinuation of chemotherapy, patients randomized to receive Avastin continued to receive Avastin alone until disease progression or until unacceptable toxicity. The trial excluded patients with predominant squamous histology (mixed cell type tumors only), CNS metastasis, gross hemoptysis (1/2 teaspoon or more of red blood), unstable angina, or receiving therapeutic anticoagulation. The demographics of the safety population were similar to the demographics of the efficacy population.

Only Grades 3-5 non-hematologic and Grades 4-5 hematologic adverse reactions were collected. Grades 3-5 non-hematologic and Grades 4-5 hematologic adverse reactions occurring at a higher incidence (≥ 2%) in patients receiving Avastin with paclitaxel and carboplatin compared with patients receiving chemotherapy alone were neutropenia (27% vs. 17%), fatigue (16% vs. 13%), hypertension (8% vs. 0.7%), infection without neutropenia (7% vs. 3%), venous thromboembolism (5% vs. 3%), febrile neutropenia (5% vs. 2%), pneumonitis/pulmonary infiltrates (5% vs. 3%), infection with Grade 3 or 4 neutropenia (4% vs. 2%), hyponatremia (4% vs. 1%), headache (3% vs. 1%) and proteinuria (3% vs. 0%).

Recurrent Glioblastoma

The safety of Avastin was evaluated in a multicenter, randomized, open-label study (EORTC 26101) in patients with recurrent GBM following radiotherapy and temozolomide of whom 278 patients received at least one dose of Avastin and are considered safety evaluable [see Clinical Studies (14.4)]. Patients were randomized (2:1) to receive Avastin (10 mg/kg every 2 weeks) with lomustine or lomustine alone until disease progression or unacceptable toxicity. The demographics of the safety population were similar to the demographics of the efficacy population. In the Avastin with lomustine arm, 22% of patients discontinued treatment due to adverse reactions compared with 10% of patients in the lomustine arm. In patients receiving Avastin with lomustine, the adverse reaction profile was similar to that observed in other approved indications.

Metastatic Renal Cell Carcinoma

The safety of Avastin was evaluated in 337 patients who received at least one dose of Avastin in a multicenter, double-blind study (BO17705) in patients with mRCC. Patients who had undergone a nephrectomy were randomized (1:1) to receive either Avastin (10 mg/kg every 2 weeks) or placebo with interferon alfa [see Clinical Studies (14.5)]. Patients were treated until disease progression or unacceptable toxicity. The demographics of the safety population were similar to the demographics of the efficacy population.

Grades 3-5 adverse reactions occurring at a higher incidence (>2%) were fatigue (13% vs. 8%), asthenia (10% vs. 7%), proteinuria (7% vs. 0%), hypertension (6% vs. 1%; including hypertension and hypertensive crisis), and hemorrhage (3% vs. 0.3%; including epistaxis, small intestinal hemorrhage, aneurysm ruptured, gastric ulcer hemorrhage, gingival bleeding, hemoptysis, hemorrhage intracranial, large intestinal hemorrhage, respiratory tract hemorrhage, and traumatic hematoma). Adverse reactions are presented in Table 3.

Table 3: Grades 1-5 Adverse Reactions Occurring at Higher Incidence (≥5%) of Patients Receiving Avastin vs. Placebo with Interferon Alfa in Study BO17705
Adverse Reaction [NCI-CTC version 3] | Avastin with Interferon Alfa (N=337) | Placebo with Interferon Alfa (N=304)
Metabolism and nutrition
Decreased appetite | 36% | 31%
Weight loss | 20% | 15%
General
Fatigue | 33% | 27%
Vascular
Hypertension | 28% | 9%
Respiratory, thoracic and mediastinal
Epistaxis | 27% | 4%
Dysphonia | 5% | 0%
Nervous system
Headache | 24% | 16%
Gastrointestinal
Diarrhea | 21% | 16%
Renal and urinary
Proteinuria | 20% | 3%
Musculoskeletal and connective tissue
Myalgia | 19% | 14%
Back pain | 12% | 6%

The following adverse reactions were reported at a 5-fold greater incidence in patients receiving Avastin with interferon-alfa compared to patients receiving placebo with interferon-alfa and not represented in Table 3: gingival bleeding (13 patients vs. 1 patient); rhinitis (9 vs. 0); blurred vision (8 vs. 0); gingivitis (8 vs. 1); gastroesophageal reflux disease (8 vs. 1); tinnitus (7 vs. 1); tooth abscess (7 vs. 0); mouth ulceration (6 vs. 0); acne (5 vs. 0); deafness (5 vs. 0); gastritis (5 vs. 0); gingival pain (5 vs. 0) and pulmonary embolism (5 vs. 1).

Persistent, Recurrent, or Metastatic Cervical Cancer

The safety of Avastin was evaluated in 218 patients who received at least one dose of Avastin in a multicenter study (GOG-0240) in patients with persistent, recurrent, or metastatic cervical cancer[see Clinical Studies (14.6)]. Patients were randomized (1:1:1:1) to receive paclitaxel and cisplatin with or without Avastin (15 mg/kg every 3 weeks), or paclitaxel and topotecan with or without Avastin (15 mg/kg every 3 weeks). The demographics of the safety population were similar to the demographics of the efficacy population.

Grades 3-4 adverse reactions occurring at a higher incidence (≥ 2%) in 218 patients receiving Avastin with chemotherapy compared to 222 patients receiving chemotherapy alone were abdominal pain (12% vs. 10%), hypertension (11% vs. 0.5%), thrombosis (8% vs. 3%), diarrhea (6% vs. 3%), anal fistula (4% vs. 0%), proctalgia (3% vs. 0%), urinary tract infection (8% vs. 6%), cellulitis (3% vs. 0.5%), fatigue (14% vs. 10%), hypokalemia (7% vs. 4%), hyponatremia (4% vs. 1%), dehydration (4% vs. 0.5%), neutropenia (8% vs. 4%), lymphopenia (6% vs. 3%), back pain (6% vs. 3%), and pelvic pain (6% vs. 1%). Adverse reactions are presented in Table 4.

Table 4: Grades 1-4 Adverse Reactions Occurring at Higher Incidence (≥ 5%) in Patients Receiving Avastin with Chemotherapy vs. Chemotherapy Alone in Study GOG-0240
Adverse Reaction [NCI-CTC version 3] | Avastin with Chemotherapy (N=218) | Chemotherapy (N=222)
General
Fatigue | 80% | 75%
Peripheral edema | 15% | 22%
Metabolism and nutrition
Decreased appetite | 34% | 26%
Hyperglycemia | 26% | 19%
Hypomagnesemia | 24% | 15%
Weight loss | 21% | 7%
Hyponatremia | 19% | 10%
Hypoalbuminemia | 16% | 11%
Vascular
Hypertension | 29% | 6%
Thrombosis | 10% | 3%
Infections
Urinary tract infection | 22% | 14%
Infection | 10% | 5%
Nervous system
Headache | 22% | 13%
Dysarthria | 8% | 1%
Psychiatric
Anxiety | 17% | 10%
Respiratory, thoracic and mediastinal
Epistaxis | 17% | 1%
Renal and urinary
Increased blood creatinine | 16% | 10%
Proteinuria | 10% | 3%
Gastrointestinal
Stomatitis | 15% | 10%
Proctalgia | 6% | 1%
Anal fistula | 6% | 0%
Reproductive system and breast
Pelvic pain | 14% | 8%
Hematology
Neutropenia | 12% | 6%
Lymphopenia | 12% | 5%

Epithelial Ovarian, Fallopian Tube or Primary Peritoneal Cancer

Stage III or IV Following Initial Surgical Resection

The safety of Avastin was evaluated in GOG-0218, a multicenter, randomized, double-blind, placebo controlled, three arm study, which evaluated the addition of Avastin to carboplatin and paclitaxel for the treatment of patients with stage III or IV epithelial ovarian, fallopian tube or primary peritoneal cancer following initial surgical resection [see Clinical Studies (14.7)]. Patients were randomized (1:1:1) to carboplatin and paclitaxel without Avastin (CPP), carboplatin and paclitaxel with Avastin for up to six cycles (CPB15), or carboplatin and paclitaxel with Avastin for six cycles followed by Avastin as a single agent for up to 16 additional doses (CPB15+). Avastin was given at 15 mg/kg every three weeks. On this trial, 1215 patients received at least one dose of Avastin. The demographics of the safety population were similar to the demographics of the efficacy population.

Grades 3-4 adverse reactions occurring at a higher incidence (≥2%) in either of the Avastin arms versus the control arm were fatigue (CPB15+ - 9%, CPB15 - 6%, CPP - 6%), hypertension (CPB15+ - 10%, CPB15 - 6%, CPP - 2%), thrombocytopenia (CPB15+ - 21%, CPB15 - 20%, CPP - 15%) and leukopenia (CPB15+ - 51%, CPB15 - 53%, CPP - 50%). Adverse reactions are presented in Table 5.

Table 5: Grades 1-5 Adverse Reactions Occurring at Higher Incidence (≥ 5%) in Patients Receiving Avastin with Chemotherapy vs. Chemotherapy Alone in GOG-0218
Adverse Reaction [NCI-CTC version 3,] | Avastin with carboplatin and paclitaxel followed by Avastin alone [CPB15+,] (N=608) | Avastin with carboplatin and paclitaxel [CPB15,] (N= 607) | Carboplatin and paclitaxel [CPP] (N= 602)
General
Fatigue | 80% | 72% | 73%
Gastrointestinal
Nausea | 58% | 53% | 51%
Diarrhea | 38% | 40% | 34%
Stomatitis | 25% | 19% | 14%
Musculoskeletal and connective tissue
Arthralgia | 41% | 33% | 35%
Pain in extremity | 25% | 19% | 17%
Muscular weakness | 15% | 13% | 9%
Nervous system
Headache | 34% | 26% | 21%
Dysarthria | 12% | 10% | 2%
Vascular
Hypertension | 32% | 24% | 14%
Respiratory, thoracic and mediastinal
Epistaxis | 31% | 30% | 9%
Dyspnea | 26% | 28% | 20%
Nasal mucosal disorder | 10% | 7% | 4%

Platinum-Resistant Recurrent Epithelial Ovarian, Fallopian Tube, or Primary Peritoneal Cancer

The safety of Avastin was evaluated in 179 patients who received at least one dose of Avastin in a multicenter, open-label study (MO22224) in which patients were randomized (1:1) to Avastin with chemotherapy or chemotherapy alone in patients with platinum resistant, recurrent epithelial ovarian, fallopian tube, or primary peritoneal cancer that recurred within < 6 months from the most recent platinum based therapy [see Clinical Studies (14.8)]. Patients were randomized to receive Avastin 10 mg/kg every 2 weeks or 15 mg/kg every 3 weeks. Patients had received no more than 2 prior chemotherapy regimens. The trial excluded patients with evidence of recto-sigmoid involvement by pelvic examination or bowel involvement on CT scan or clinical symptoms of bowel obstruction. Patients were treated until disease progression or unacceptable toxicity. Forty percent of patients on the chemotherapy alone arm received Avastin alone upon progression. The demographics of the safety population were similar to the demographics of the efficacy population.

Grades 3-4 adverse reactions occurring at a higher incidence (≥ 2%) in 179 patients receiving Avastin with chemotherapy compared to 181 patients receiving chemotherapy alone were hypertension (6.7% vs. 1.1%) and palmar-plantar erythrodysaesthesia syndrome (4.5% vs. 1.7%).

Adverse reactions are presented in Table 6.

Table 6: Grades 2–4 Adverse Reactions Occurring at Higher Incidence (≥ 5%) in Patients Receiving Avastin with Chemotherapy vs. Chemotherapy Alone in Study MO22224
Adverse Reaction [NCI-CTC version 3] | Avastin with Chemotherapy (N=179) | Chemotherapy (N=181)
Hematology
Neutropenia | 31% | 25%
Vascular
Hypertension | 19% | 6%
Nervous system
Peripheral sensory neuropathy | 18% | 7%
General
Mucosal inflammation | 13% | 6%
Renal and urinary
Proteinuria | 12% | 0.6%
Skin and subcutaneous tissue
Palmar-plantar erythrodysaesthesia | 11% | 5%
Infections
Infection | 11% | 4%
Respiratory, thoracic and mediastinal
Epistaxis | 5% | 0%

Platinum-Sensitive Recurrent Epithelial Ovarian, Fallopian Tube, or Primary Peritoneal Cancer

Study AVF4095g

The safety of Avastin was evaluated in 247 patients who received at least one dose of Avastin in a double-blind study (AVF4095g) in patients with platinum sensitive recurrent epithelial ovarian, fallopian tube or primary peritoneal cancer [see Clinical Studies (14.9]. Patients were randomized (1:1) to receive Avastin (15 mg/kg) or placebo every 3 weeks with carboplatin and gemcitabine for 6 to 10 cycles followed by Avastin or placebo alone until disease progression or unacceptable toxicity. The demographics of the safety population were similar to the demographics of the efficacy population.

Grades 3-4 adverse reactions occurring at a higher incidence (≥ 2%) in patients receiving Avastin with chemotherapy compared to placebo with chemotherapy were: thrombocytopenia (40% vs. 34%), nausea (4% vs. 1.3%), fatigue (6% vs. 4%), headache (4% vs. 0.9%), proteinuria (10% vs. 0.4%), dyspnea (4% vs. 1.7%), epistaxis (5% vs. 0.4%), and hypertension (17% vs. 0.9%). Adverse reactions are presented in Table 7.

Table 7: Grades 1–5 Adverse Reactions Occurring at a Higher Incidence (≥ 5%) in Patients Receiving Avastin with Chemotherapy vs. Placebo with Chemotherapy in Study AVF4095g
Adverse Reaction [NCI-CTC version 3] | Avastin with Carboplatin and Gemcitabine (N=247) | Placebo with Carboplatin and Gemcitabine (N=233)
General
Fatigue | 82% | 75%
Mucosal inflammation | 15% | 10%
Gastrointestinal
Nausea | 72% | 66%
Diarrhea | 38% | 29%
Stomatitis | 15% | 7%
Hemorrhoids | 8% | 3%
Gingival bleeding | 7% | 0%
Hematology
Thrombocytopenia | 58% | 51%
Respiratory, thoracic and mediastinal
Epistaxis | 55% | 14%
Dyspnea | 30% | 24%
Cough | 26% | 18%
Oropharyngeal pain | 16% | 10%
Dysphonia | 13% | 3%
Rhinorrhea | 10% | 4%
Sinus congestion | 8% | 2%
Nervous system
Headache | 49% | 30%
Dizziness | 23% | 17%
Vascular
Hypertension | 42% | 9%
Musculoskeletal and connective tissue
Arthralgia | 28% | 19%
Back pain | 21% | 13%
Psychiatric
Insomnia | 21% | 15%
Renal and urinary
Proteinuria | 20% | 3%
Injury and procedural
Contusion | 17% | 9%
Infections
Sinusitis | 15% | 9%

Study GOG-0213

The safety of Avastin was evaluated in an open-label, controlled study (GOG-0213) in 325 patients with platinum-sensitive recurrent epithelial ovarian, fallopian tube, or primary peritoneal cancer, who have not received more than one previous regimen of chemotherapy[see Clinical Studies (14.9)]. Patients were randomized (1:1) to receive carboplatin and paclitaxel for 6 to 8 cycles or Avastin (15 mg/kg every 3 weeks) with carboplatin and paclitaxel for 6 to 8 cycles followed by Avastin as a single agent until disease progression or unacceptable toxicity. The demographics of the safety population were similar to the demographics of the efficacy population.

Grades 3-4 adverse reactions occurring at a higher incidence (≥ 2%) in patients receiving Avastin with chemotherapy compared to chemotherapy alone were: hypertension (11% vs. 0.6%), fatigue (8% vs. 3%), febrile neutropenia (6% vs. 3%), proteinuria (8% vs. 0%), abdominal pain (6% vs. 0.9%), hyponatremia (4% vs. 0.9%), headache (3% vs. 0.9%), and pain in extremity (3% vs. 0%).

Adverse reactions are presented in Table 8.

Table 8: Grades 1–5 Adverse Reactions Occurring at Higher Incidence (≥ 5%) in Patients Receiving Avastin with Chemotherapy vs. Chemotherapy Alone in Study GOG-0213
Adverse Reaction [NCI-CTC version 3] | Avastin with Carboplatin and Paclitaxel (N=325) | Carboplatin and Paclitaxel (N=332)
Musculoskeletal and connective tissue
Arthralgia | 45% | 30%
Myalgia | 29% | 18%
Pain in extremity | 25% | 14%
Back pain | 17% | 10%
Muscular weakness | 13% | 8%
Neck pain | 9% | 0%
Vascular
Hypertension | 42% | 3%
Gastrointestinal
Diarrhea | 39% | 32%
Abdominal pain | 33% | 28%
Vomiting | 33% | 25%
Stomatitis | 33% | 16%
Nervous system
Headache | 38% | 20%
Dysarthria | 14% | 2%
Dizziness | 13% | 8%
Metabolism and nutrition
Decreased appetite | 35% | 25%
Hyperglycemia | 31% | 24%
Hypomagnesemia | 27% | 17%
Hyponatremia | 17% | 6%
Weight loss | 15% | 4%
Hypocalcemia | 12% | 5%
Hypoalbuminemia | 11% | 6%
Hyperkalemia | 9% | 3%
Respiratory, thoracic and mediastinal
Epistaxis | 33% | 2%
Dyspnea | 30% | 25%
Cough | 30% | 17%
Rhinitis allergic | 17% | 4%
Nasal mucosal disorder | 14% | 3%
Skin and subcutaneous tissue
Exfoliative rash | 23% | 16%
Nail disorder | 10% | 2%
Dry skin | 7% | 2%
Renal and urinary
Proteinuria | 17% | 1%
Increased blood creatinine | 13% | 5%
Hepatic
Increased aspartate aminotransferase | 15% | 9%
General
Chest pain | 8% | 2%
Infections
Sinusitis | 7% | 2%

Hepatocellular Carcinoma (HCC)

The safety of Avastin in combination with atezolizumab was evaluated in IMbrave150, a multicenter, international, randomized, open-label trial in patients with locally advanced or metastatic or unresectable hepatocellular carcinoma who have not received prior systemic treatment [see Clinical Studies (14.10)]. Patients received 1,200 mg of atezolizumab intravenously followed by 15 mg/kg Avastin (n=329) every 3 weeks, or 400 mg of sorafenib (n=156) given orally twice daily, until disease progression or unacceptable toxicity. The median duration of exposure to Avastin was 6.9 months (range: 0-16 months) and to atezolizumab was 7.4 months (range: 0-16 months).

Fatal adverse reactions occurred in 4.6% of patients in the Avastin and atezolizumab arm. The most common adverse reactions leading to death were gastrointestinal and esophageal varices hemorrhage (1.2%) and infections (1.2%).

Serious adverse reactions occurred in 38% of patients in the Avastin and atezolizumab arm. The most frequent serious adverse reactions (≥ 2%) were gastrointestinal hemorrhage (7%), infections (6%), and pyrexia (2.1%).

Adverse reactions leading to discontinuation of Avastin occurred in 15% of patients in the Avastin and atezolizumab arm. The most common adverse reactions leading to Avastin discontinuation were hemorrhages (4.9%), including bleeding varicose vein, hemorrhage and gastrointestinal, subarachnoid, and pulmonary hemorrhages; and increased transaminases or bilirubin (0.9%).

Adverse reactions leading to interruption of Avastin occurred in 46% of patients in the Avastin and atezolizumab arm; the most common (≥ 2%) were proteinuria (6%); infections (6%); hypertension (6%); liver function laboratory abnormalities including increased transaminases, bilirubin, or alkaline phosphatase (4.6%); gastrointestinal hemorrhages (3%); thrombocytopenia/decreased platelet count (4.3%); and pyrexia (2.4%).

Tables 9 and 10 summarize adverse reactions and laboratory abnormalities, respectively, in patients who received Avastin and atezolizumab in IMbrave150.

Table 9: Adverse Reactions Occurring in ≥10% of Patients with HCC Receiving Avastin in IMbrave150
Adverse Reaction | Avastin in combination with atezolizumab (n = 329) |  | Sorafenib (n=156)
Adverse Reaction | All Grades [Includes fatigue and asthenia] (%) | Grades 3–4 (%) | All Grades (%) | Grades 3–4 (%)
Vascular Disorders
Hypertension | 30 | 15 | 24 | 12
General Disorders and Administration Site Conditions
Fatigue/asthenia | 26 | 2 | 32 | 6
Pyrexia | 18 | 0 | 10 | 0
Renal and Urinary Disorders
Proteinuria | 20 | 3 | 7 | 0.6
Investigations
Weight Decreased | 11 | 0 | 10 | 0
Skin and Subcutaneous Tissue Disorders
Pruritus | 19 | 0 | 10 | 0
Rash | 12 | 0 | 17 | 2.6
Gastrointestinal Disorders
Diarrhea | 19 | 1.8 | 49 | 5
Constipation | 13 | 0 | 14 | 0
Abdominal Pain | 12 | 0 | 17 | 0
Nausea | 12 | 0 | 16 | 0
Vomiting | 10 | 0 | 8 | 0
Metabolism and Nutrition Disorders
Decreased Appetite | 18 | 1.2 | 24 | 3.8
Respiratory, Thoracic and Mediastinal Disorders
Cough | 12 | 0 | 10 | 0
Epistaxis | 10 | 0 | 4.5 | 0
Injury, Poisoning and Procedural Complications
Infusion Related Reaction | 11 | 2.4 | 0 | 0
^2 Graded per NCI CTCAE v4.0

Table 10: Laboratory Abnormalities Worsening from Baseline Occurring in ≥20% of Patients with HCC Receiving Avastin in IMbrave150
Laboratory Abnormality | Avastin in combination with atezolizumab (n=329) |  | Sorafenib (n=156)
Laboratory Abnormality | All Grades [Graded per NCI CTCAE v4.0] (%) | Grades 3–4 (%) | All Grades (%) | Grades 3–4 (%)
Chemistry
Increased AST | 86 | 16 | 90 | 16
Increased Alkaline Phosphatase | 70 | 4 | 76 | 4.6
Increased ALT | 62 | 8 | 70 | 4.6
Decreased Albumin | 60 | 1.5 | 54 | 0.7
Decreased Sodium | 54 | 13 | 49 | 9
Increased Glucose | 48 | 9 | 43 | 4.6
Decreased Calcium | 30 | 0.3 | 35 | 1.3
Decreased Phosphorus | 26 | 4.7 | 58 | 16
Increased Potassium | 23 | 1.9 | 16 | 2
Hypomagnesemia | 22 | 0 | 22 | 0
Hematology
Decreased Platelet | 68 | 7 | 63 | 4.6
Decreased Lymphocytes | 62 | 13 | 58 | 11
Decreased Hemoglobin | 58 | 3.1 | 62 | 3.9
Increased Bilirubin | 57 | 8 | 59 | 14
Decreased Leukocyte | 32 | 3.4 | 29 | 1.3
Decreased Neutrophil | 23 | 2.3 | 16 | 1.1
Each test incidence is based on the number of patients who had both baseline and at least one on-study laboratory measurement available: Avastin plus atezolizumab (222-323) and sorafenib (90-153) NA = Not applicable.

6.2 Immunogenicity

As with all therapeutic proteins, there is a potential for immunogenicity. The detection of antibody formation is highly dependent on the sensitivity and the specificity of the assay. Additionally, the observed incidence of antibody (including neutralizing antibody) positivity in an assay may be influenced by several factors, including assay methodology, sample handling, timing of sample collection, concomitant medications, and underlying disease. For these reasons, comparison of the incidence of antibodies to bevacizumab in the studies described below with the incidence of antibodies in other studies or to other bevacizumab products may be misleading.

In clinical studies for adjuvant treatment of a solid tumor, 0.6% (14/2233) of patients tested positive for treatment-emergent anti-bevacizumab antibodies as detected by an electrochemiluminescent (ECL) based assay. Among these 14 patients, three tested positive for neutralizing antibodies against bevacizumab using an enzyme-linked immunosorbent assay (ELISA). The clinical significance of these anti-bevacizumab antibodies is not known.

6.3 Postmarketing Experience

The following adverse reactions have been identified during postapproval use of Avastin. Because these reactions are reported voluntarily from a population of uncertain size, it is not always possible to reliably estimate their frequency or establish a causal relationship to drug exposure.

General: Polyserositis

Cardiovascular: Pulmonary hypertension, Mesenteric venous occlusion

Gastrointestinal: Gastrointestinal ulcer, Intestinal necrosis, Anastomotic ulceration

Hemic and lymphatic: Pancytopenia

Hepatobiliary disorders: Gallbladder perforation

Musculoskeletal and Connective Tissue Disorders: Osteonecrosis of the jaw

Renal: Renal thrombotic microangiopathy (manifested as severe proteinuria)

Respiratory: Nasal septum perforation

Vascular: Arterial (including aortic) aneurysms, dissections, and rupture

7 DRUG INTERACTIONS

Effects of Avastin on Other Drugs

No clinically meaningful effect on the pharmacokinetics of irinotecan or its active metabolite SN38, interferon alfa, carboplatin or paclitaxel was observed when Avastin was administered in combination with these drugs; however, 3 of the 8 patients receiving Avastin with paclitaxel and carboplatin had lower paclitaxel exposure after four cycles of treatment (at Day 63) than those at Day 0, while patients receiving paclitaxel and carboplatin alone had a greater paclitaxel exposure at Day 63 than at Day 0.

8 USE IN SPECIFIC POPULATIONS

8.1 Pregnancy

Risk Summary

Based on findings from animal studies and its mechanism of action [see Clinical Pharmacology (12.1)], Avastin may cause fetal harm in pregnant women. Limited postmarketing reports describe cases of fetal malformations with use of Avastin in pregnancy; however, these reports are insufficient to determine drug-associated risks. In animal reproduction studies, intravenous administration of bevacizumab to pregnant rabbits every 3 days during organogenesis at doses approximately 1 to 10 times the clinical dose of 10 mg/kg produced fetal resorptions, decreased maternal and fetal weight gain and multiple congenital malformations including corneal opacities and abnormal ossification of the skull and skeleton including limb and phalangeal defects (see Data). Furthermore, animal models link angiogenesis and VEGF and VEGFR2 to critical aspects of female reproduction, embryofetal development, and postnatal development. Advise pregnant women of the potential risk to a fetus.

In the U.S. general population, the estimated background risk of major birth defects and miscarriage in clinically recognized pregnancies is 2% to 4% and 15% to 20%, respectively.

Data

Animal Data

Pregnant rabbits dosed with 10 mg/kg to 100 mg/kg bevacizumab (approximately 1 to 10 times the clinical dose of 10 mg/kg) every three days during the period of organogenesis (gestation day 6–18) exhibited decreases in maternal and fetal body weights and increased number of fetal resorptions. There were dose-related increases in the number of litters containing fetuses with any type of malformation (42% for the 0 mg/kg dose, 76% for the 30 mg/kg dose, and 95% for the 100 mg/kg dose) or fetal alterations (9% for the 0 mg/kg dose, 15% for the 30 mg/kg dose, and 61% for the 100 mg/kg dose). Skeletal deformities were observed at all dose levels, with some abnormalities including meningocele observed only at the 100 mg/kg dose level. Teratogenic effects included: reduced or irregular ossification in the skull, jaw, spine, ribs, tibia and bones of the paws; fontanel, rib and hindlimb deformities; corneal opacity; and absent hindlimb phalanges.

8.2 Lactation

Risk Summary

No data are available regarding the presence of bevacizumab in human milk, the effects on the breast fed infant, or the effects on milk production. Human IgG is present in human milk, but published data suggest that breast milk antibodies do not enter the neonatal and infant circulation in substantial amounts. Because of the potential for serious adverse reactions in breastfed infants, advise women not to breastfeed during treatment with Avastin and for 6 months after the last dose.

8.3 Females and Males of Reproductive Potential

Contraception

Females

Avastin may cause fetal harm when administered to a pregnant woman [see Use in Specific Populations (8.1)]. Advise females of reproductive potential to use effective contraception during treatment with Avastin and for 6 months after the last dose.

Infertility

Females

Avastin increases the risk of ovarian failure and may impair fertility. Inform females of reproductive potential of the risk of ovarian failure prior to the first-dose of Avastin. Long-term effects of Avastin on fertility are not known.

In a clinical study of 179 premenopausal women randomized to receive chemotherapy with or without Avastin, the incidence of ovarian failure was higher in patients who received Avastin with chemotherapy (34%) compared to patients who received chemotherapy alone (2%). After discontinuing Avastin with chemotherapy, recovery of ovarian function occurred in 22% of these patients [see Warnings and Precautions (5.11), Adverse Reactions (6.1)].

8.4 Pediatric Use

The safety and effectiveness of Avastin in pediatric patients have not been established.

In published literature reports, cases of non-mandibular osteonecrosis have been observed in patients under the age of 18 years who received Avastin. Avastin is not approved for use in patients under the age of 18 years.

Antitumor activity was not observed among eight pediatric patients with relapsed GBM who received bevacizumab and irinotecan. Addition of Avastin to standard of care did not result in improved event-free survival in pediatric patients enrolled in two randomized clinical studies, one in high grade glioma (n= 121) and one in metastatic rhabdomyosarcoma or non-rhabdomyosarcoma soft tissue sarcoma (n= 154).

Based on the population pharmacokinetics analysis of data from 152 pediatric and young adult patients with cancer (7 months to 21 years of age), bevacizumab clearance normalized by body weight in pediatrics was comparable to that in adults.

Juvenile Animal Toxicity Data

Juvenile cynomolgus monkeys with open growth plates exhibited physeal dysplasia following 4 to 26 weeks exposure at 0.4 to 20 times the recommended human dose (based on mg/kg and exposure). The incidence and severity of physeal dysplasia were dose-related and were partially reversible upon cessation of treatment.

8.5 Geriatric Use

In an exploratory pooled analysis of 1745 patients from five randomized, controlled studies, 35% of patients were ≥ 65 years old. The overall incidence of ATE was increased in all patients receiving Avastin with chemotherapy as compared to those receiving chemotherapy alone, regardless of age; however, the increase in the incidence of ATE was greater in patients ≥ 65 years (8% vs. 3%) as compared to patients < 65 years (2% vs. 1%) [see Warnings and Precautions (5.4)].

11 DESCRIPTION

Bevacizumab is a vascular endothelial growth factor inhibitor. Bevacizumab is a recombinant humanized monoclonal IgG1 antibody that contains human framework regions and murine complementarity-determining regions. Bevacizumab has an approximate molecular weight of 149 kDa. Bevacizumab is produced in a mammalian cell (Chinese Hamster Ovary) expression system.

Avastin (bevacizumab) injection is a sterile, preservative-free, clear to slightly opalescent, colorless to pale brown solution in a single-dose vial for intravenous use. Avastin contains bevacizumab at a concentration of 25 mg/mL in either a 100 mg/4 mL or 400 mg/16 mL single-dose vial.

Each mL of solution contains 25 mg bevacizumab, α,α-trehalose dihydrate (60 mg), polysorbate 20 (0.4 mg), sodium phosphate dibasic, anhydrous (1.2 mg), sodium phosphate monobasic, monohydrate (5.8 mg), and Water for Injection, USP. The pH is 6.2.

12 CLINICAL PHARMACOLOGY

12.1 Mechanism of Action

Bevacizumab binds VEGF and prevents the interaction of VEGF to its receptors (Flt-1 and KDR) on the surface of endothelial cells. The interaction of VEGF with its receptors leads to endothelial cell proliferation and new blood vessel formation in in vitro models of angiogenesis. Administration of bevacizumab to xenotransplant models of colon cancer in nude (athymic) mice caused reduction of microvascular growth and inhibition of metastatic disease progression.

12.3 Pharmacokinetics

The pharmacokinetic profile of bevacizumab was assessed using an assay that measures total serum bevacizumab concentrations (i.e., the assay did not distinguish between free bevacizumab and bevacizumab bound to VEGF ligand). Based on a population pharmacokinetic analysis of 491 patients who received 1 to 20 mg/kg of Avastin every week, every 2 weeks, or every 3 weeks, bevacizumab pharmacokinetics are linear and the predicted time to reach more than 90% of steady state concentration is 84 days. The accumulation ratio following a dose of 10 mg/kg once every 2 weeks is 2.8.

Population simulations of bevacizumab exposures provide a median trough concentration of 80.3 mcg/mL on Day 84 (10th, 90th percentile: 45, 128) following a dose of 5 mg/kg once every two weeks.

Distribution

The mean (% coefficient of variation [CV%]) central volume of distribution is 2.9 (22%) L.

Elimination

The mean (CV%) clearance is 0.23 (33) L/day. The estimated half-life is 20 days (11 to 50 days).

Specific Populations

The clearance of bevacizumab varied by body weight, sex, and tumor burden. After correcting for body weight, males had a higher bevacizumab clearance (0.26 L/day vs. 0.21 L/day) and a larger central volume of distribution (3.2 L vs. 2.7 L) than females. Patients with higher tumor burden (at or above median value of tumor surface area) had a higher bevacizumab clearance (0.25 L/day vs. 0.20 L/day) than patients with tumor burdens below the median. In Study AVF2107g, there was no evidence of lesser efficacy (hazard ratio for overall survival) in males or patients with higher tumor burden treated with Avastin as compared to females and patients with low tumor burden.

13 NONCLINICAL TOXICOLOGY

13.1 Carcinogenesis, Mutagenesis, Impairment of Fertility

No studies have been conducted to assess potential of bevacizumab for carcinogenicity or mutagenicity.

Bevacizumab may impair fertility. Female cynomolgus monkeys treated with 0.4 to 20 times the recommended human dose of bevacizumab exhibited arrested follicular development or absent corpora lutea, as well as dose-related decreases in ovarian and uterine weights, endometrial proliferation, and the number of menstrual cycles. Following a 4- or 12-week recovery period, there was a trend suggestive of reversibility. After the 12-week recovery period, follicular maturation arrest was no longer observed, but ovarian weights were still moderately decreased. Reduced endometrial proliferation was no longer observed at the 12-week recovery time point; however, decreased uterine weight, absent corpora lutea, and reduced number of menstrual cycles remained evident.

13.2 Animal Toxicology and/or Pharmacology

Rabbits dosed with bevacizumab exhibited reduced wound healing capacity. Using full-thickness skin incision and partial thickness circular dermal wound models, bevacizumab dosing resulted in reductions in wound tensile strength, decreased granulation and re-epithelialization, and delayed time to wound closure.

14 CLINICAL STUDIES

14.1 Metastatic Colorectal Cancer

Study AVF2107g

The safety and efficacy of Avastin was evaluated in a double-blind, active-controlled study [AVF2107g (NCT00109070)] in 923 patients with previously untreated mCRC who were randomized (1:1:1) to placebo with bolus-IFL (irinotecan 125 mg/m^2, fluorouracil 500 mg/m^2, and leucovorin 20 mg/m^2 given once weekly for 4 weeks every 6 weeks), Avastin (5 mg/kg every 2 weeks) with bolus-IFL, or Avastin (5 mg/kg every 2 weeks) with fluorouracil and leucovorin. Enrollment to the Avastin with fluorouracil and leucovorin arm was discontinued after enrollment of 110 patients in accordance with the protocol-specified adaptive design. Avastin was continued until disease progression or unacceptable toxicity or for a maximum of 96 weeks. The main outcome measure was overall survival (OS).

The median age was 60 years; 60% were male, 79% were White, 57% had an ECOG performance status of 0, 21% had a rectal primary and 28% received prior adjuvant chemotherapy. The dominant site of disease was extra-abdominal in 56% of patients and was the liver in 38% of patients.

The addition of Avastin improved survival across subgroups defined by age (< 65 years, ≥ 65 years) and sex. Results are presented in Table 11 and Figure 1.

Table 11: Efficacy Results in Study AVF2107g
Efficacy Parameter | Avastin with bolus-IFL (N=402) | Placebo with bolus-IFL (N=411)
Overall Survival
Median, in months | 20.3 | 15.6
Hazard ratio (95% CI) | 0.66 (0.54, 0.81)
p-value [by stratified log-rank test.] | < 0.001
Progression-Free Survival
Median, in months | 10.6 | 6.2
Hazard ratio (95% CI) | 0.54 (0.45, 0.66)
p-value | < 0.001
Overall Response Rate
Rate (%) | 45% | 35%
p-value [by χ^2 test] | < 0.01
Duration of Response
Median, in months | 10.4 | 7.1

Figure 1: Kaplan-Meier Curves for Duration of Survival in Metastatic Colorectal Cancer in Study AVF2107g

Among the 110 patients randomized to Avastin with fluorouracil and leucovorin, median OS was 18.3 months, median progression-free survival (PFS) was 8.8 months, overall response rate (ORR) was 39%, and median duration of response was 8.5 months.

Study E3200

The safety and efficacy of Avastin were evaluated in a randomized, open-label, active-controlled study [E3200 (NCT00025337)] in 829 patients who were previously treated with irinotecan and fluorouracil for initial therapy for metastatic disease or as adjuvant therapy. Patients were randomized (1:1:1) to FOLFOX4 (Day 1: oxaliplatin 85 mg/m^2 and leucovorin 200 mg/m^2 concurrently, then fluorouracil 400 mg/m^2 bolus followed by 600 mg/m^2 continuously; Day 2: leucovorin 200 mg/m^2, then fluorouracil 400 mg/m^2 bolus followed by 600 mg/m^2 continuously; every 2 weeks), Avastin (10 mg/kg every 2 weeks prior to FOLFOX4 on Day 1) with FOLFOX4, or Avastin alone (10 mg/kg every 2 weeks). Avastin was continued until disease progression or unacceptable toxicity. The main outcome measure was OS.

The Avastin alone arm was closed to accrual after enrollment of 244 of the planned 290 patients following a planned interim analysis by the data monitoring committee based on evidence of decreased survival compared to FOLFOX4 alone.

The median age was 61 years; 60% were male, 87% were White, 49% had an ECOG performance status of 0, 26% received prior radiation therapy, and 80% received prior adjuvant chemotherapy, 99% received prior irinotecan with or without fluorouracil for metastatic disease, and 1% received prior irinotecan and fluorouracil as adjuvant therapy.

The addition of Avastin to FOLFOX4 resulted in significantly longer survival as compared to FOLFOX4 alone; median OS was 13.0 months vs. 10.8 months [hazard ratio (HR) 0.75 (95% CI: 0.63, 0.89), p-value of 0.001 stratified log-rank test] with clinical benefit seen in subgroups defined by age (< 65 years, ≥ 65 years) and sex. PFS and ORR based on investigator assessment were higher in patients receiving Avastin with FOLFOX4.

Study TRC-0301

The activity of Avastin with fluorouracil (as bolus or infusion) and leucovorin was evaluated in a single arm study [TRC-0301 (NCT00066846)] enrolling 339 patients with mCRC with disease progression following both irinotecan- and oxaliplatin-based chemotherapy. Seventy-three percent of patients received concurrent bolus fluorouracil and leucovorin. One objective partial response was verified in the first 100 evaluable patients for an ORR of 1% (95% CI: 0%, 5.5%).

Study ML18147

The safety and efficacy of Avastin were evaluated in a prospective, randomized, open-label, multinational, controlled study [ML18147 (NCT00700102)] in 820 patients with histologically confirmed mCRC who had progressed on a first-line Avastin containing regimen. Patients were excluded if they progressed within 3 months of initiating first-line chemotherapy and if they received Avastin for less than 3 consecutive months in the first-line setting. Patients were randomized (1:1) within 3 months after discontinuing Avastin as first-line treatment to receive fluoropyrimidine-irinotecan- or fluoropyrimidine-oxaliplatin-based chemotherapy with or without Avastin (5 mg/kg every 2 weeks or 7.5 mg/kg every 3 weeks). The choice of second-line treatment was contingent upon first-line chemotherapy. Second-line treatment was administered until progressive disease or unacceptable toxicity. The main outcome measure was OS. A secondary outcome measure was ORR.

The median age was 63 years (21 to 84 years); 64% were male, 52% had an ECOG performance status of 1, 44% had an ECOG performance status of 0, 58% received irinotecan-based therapy as first-line treatment, 55% progressed on first-line treatment within 9 months, and 77% received their last dose of Avastin as first-line treatment within 42 days of being randomized. Second-line chemotherapy regimens were generally balanced between each arm.

The addition of Avastin to fluoropyrimidine-based chemotherapy resulted in a statistically significant prolongation of OS and PFS. There was no significant difference in ORR. Results are presented in Table 12 and Figure 2.

Table 12: Efficacy Results in Study ML18147
Efficacy Parameter | Avastin with Chemotherapy (N=409) | Chemotherapy (N=411)
Overall Survival [p=0.0057 by unstratified log-rank test.]
Median, in months | 11.2 | 9.8
Hazard ratio (95% CI) | 0.81 (0.69, 0.94)
Progression-Free Survival [p-value < 0.0001 by unstratified log-rank test.]
Median, in months | 5.7 | 4.0
Hazard ratio (95% CI) | 0.68 (0.59, 0.78)

Figure 2: Kaplan-Meier Curves for Duration of Survival in Metastatic Colorectal Cancer in Study ML18147

14.2 Lack of Efficacy in Adjuvant Treatment of Colon Cancer

Lack of efficacy of Avastin as an adjunct to standard chemotherapy for the adjuvant treatment of colon cancer was determined in two randomized, open-label, multicenter clinical studies.

The first study [BO17920 (NCT00112918)] was conducted in 3451 patients with high-risk stage II and III colon cancer, who had undergone surgery for colon cancer with curative intent. Patients were randomized to receive Avastin at a dose equivalent to 2.5 mg/kg/week on either a 2-weekly schedule with FOLFOX4 (N=1155) or on a 3-weekly schedule with XELOX (N=1145) or FOLFOX4 alone (N=1151). The main outcome measure was disease free survival (DFS) in patients with stage III colon cancer.

The median age was 58 years; 54% were male, 84% were White and 29% were ≥ 65 years. Eighty-three percent had stage III disease.

The addition of Avastin to chemotherapy did not improve DFS. As compared to FOLFOX4 alone, the proportion of stage III patients with disease recurrence or with death due to disease progression were numerically higher for patients receiving Avastin with FOLFOX4 or with XELOX. The hazard ratios for DFS were 1.17 (95% CI: 0.98,1.39) for Avastin with FOLFOX4 versus FOLFOX4 alone and 1.07 (95% CI: 0.90, 1.28) for Avastin with XELOX versus FOLFOX4 alone. The hazard ratios for OS were 1.31 (95% CI: 1.03, 1.67) and 1.27 (95% CI: 1, 1.62) for the comparison of Avastin with FOLFOX4 versus FOLFOX4 alone and Avastin with XELOX versus FOLFOX4 alone, respectively. Similar lack of efficacy for DFS was observed in the Avastin-containing arms compared to FOLFOX4 alone in the high-risk stage II cohort.

In a second study [NSABP-C-08 (NCT00096278)], patients with stage II and III colon cancer who had undergone surgery with curative intent, were randomized to receive either Avastin administered at a dose equivalent to 2.5 mg/kg/week with mFOLFOX6 (N=1354) or mFOLFOX6 alone (N=1356). The median age was 57 years, 50% were male and 87% White. Seventy-five percent had stage III disease. The main outcome was DFS among stage III patients. The HR for DFS was 0.92 (95% CI: 0.77, 1.10). OS was not significantly improved with the addition of Avastin to mFOLFOX6 [HR 0.96 (95% CI: 0.75,1.22)].

14.3 First-Line Non–Squamous Non–Small Cell Lung Cancer

Study E4599

The safety and efficacy of Avastin as first-line treatment of patients with locally advanced, metastatic, or recurrent non–squamous NSCLC was studied in a single, large, randomized, active-controlled, open-label, multicenter study [E4599 (NCT00021060)]. A total of 878 chemotherapy-naïve patients with locally advanced, metastatic or recurrent non–squamous NSCLC were randomized (1:1) to receive six 21-day cycles of paclitaxel (200 mg/m^2) and carboplatin (AUC 6) with or without Avastin 15 mg/kg. After completing or discontinuing chemotherapy, patients randomized to receive Avastin continued to receive Avastin alone until disease progression or until unacceptable toxicity. The trial excluded patients with predominant squamous histology (mixed cell type tumors only), CNS metastasis, gross hemoptysis (1/2 teaspoon or more of red blood), unstable angina, or receiving therapeutic anticoagulation. The main outcome measure was duration of survival.

The median age was 63 years; 54% were male, 43% were ≥ 65 years, and 28% had ≥ 5% weight loss at study entry. Eleven percent had recurrent disease. Of the 89% with newly diagnosed NSCLC, 12% had Stage IIIB with malignant pleural effusion and 76% had Stage IV disease.

OS was statistically significantly longer for patients receiving Avastin with paclitaxel and carboplatin compared with those receiving chemotherapy alone. Median OS was 12.3 months vs. 10.3 months [HR 0.80 (95% CI: 0.68, 0.94), final p-value of 0.013, stratified log-rank test]. Based on investigator assessment which was not independently verified, patients were reported to have longer PFS with Avastin with paclitaxel and carboplatin compared to chemotherapy alone. Results are presented in Figure 3.

Figure 3: Kaplan-Meier Curves for Duration of Survival in First-Line Non-Squamous Non-Small Cell Lung Cancer in Study E4599

In an exploratory analysis across patient subgroups, the impact of Avastin on OS was less robust in the following subgroups: women [HR 0.99 (95% CI: 0.79, 1.25)], patients ≥ 65 years [HR 0.91 (95% CI: 0.72, 1.14)] and patients with ≥ 5% weight loss at study entry [HR 0.96 (95% CI: 0.73, 1.26)].

Study BO17704

The safety and efficacy of Avastin in patients with locally advanced, metastatic or recurrent non-squamous NSCLC, who had not received prior chemotherapy was studied in another randomized, double-blind, placebo-controlled study [BO17704 (NCT00806923)]. A total of 1043 patients were randomized (1:1:1) to receive cisplatin and gemcitabine with placebo, Avastin 7.5 mg/kg or Avastin 15 mg/kg. The main outcome measure was PFS. Secondary outcome measure was OS.

The median age was 58 years; 36% were female and 29% were ≥ 65 years. Eight percent had recurrent disease and 77% had Stage IV disease.

PFS was significantly higher in both Avastin-containing arms compared to the placebo arm [HR 0.75 (95% CI: 0.62, 0.91), p-value of 0.0026 for Avastin 7.5 mg/kg and HR 0.82 (95% CI: 0.68; 0.98), p-value of 0.0301 for Avastin 15 mg/kg]. The addition of Avastin to cisplatin and gemcitabine failed to demonstrate an improvement in the duration of OS [HR 0.93 (95% CI: 0.78; 1.11), p-value of 0.420 for Avastin 7.5 mg/kg and HR 1.03 (95% CI: 0.86, 1.23), p-value of 0.761 for Avastin 15 mg/kg].

14.4 Recurrent Glioblastoma

Study EORTC 26101

The safety and efficacy of Avastin were evaluated in a multicenter, randomized (2:1), open-label study in patients with recurrent GBM (EORTC 26101, NCT01290939). Patients with first progression following radiotherapy and temozolomide were randomized (2:1) to receive Avastin (10 mg/kg every 2 weeks) with lomustine (90 mg/m^2 every 6 weeks) or lomustine (110 mg/m^2 every 6 weeks) alone until disease progression or unacceptable toxicity. Randomization was stratified by World Health Organization performance status (0 vs. >0), steroid use (yes vs. no), largest tumor diameter (≤ 40 vs. > 40 mm), and institution. The main outcome measure was OS. Secondary outcome measures were investigator-assessed PFS and ORR per the modified Response Assessment in Neuro-oncology (RANO) criteria, health related quality of life (HRQoL), cognitive function, and corticosteroid use.

A total of 432 patients were randomized to receive lomustine alone (N=149) or Avastin with lomustine (N=283). The median age was 57 years; 24.8% of patients were ≥ 65 years. The majority of patients with were male (61%); 66% had a WHO performance status score > 0; and in 56% the largest tumor diameter was ≤ 40 mm. Approximately 33% of patients randomized to receive lomustine received Avastin following documented progression.

No difference in OS (HR 0.91, p -value of 0.4578) was observed between arms; therefore, all secondary outcome measures are descriptive only. PFS was longer in the Avastin with lomustine arm [HR 0.52 (95% CI: 0.41, 0.64)] with a median PFS of 4.2 months in the Avastin with lomustine arm and 1.5 months in the lomustine arm. Among the 50% of patients receiving corticosteroids at the time of randomization, a higher percentage of patients in the Avastin with lomustine arm discontinued corticosteroids (23% vs. 12%).

Study AVF3708g and Study NCI 06-C-0064E

The efficacy and safety of Avastin 10 mg/kg every 2 weeks in patients with previously treated GBM were evaluated in one single arm single center study (NCI 06-C-0064E) and a randomized noncomparative multicenter study [AVF3708g (NCT00345163)]. Response rates in both studies were evaluated based on modified WHO criteria that considered corticosteroid use. In AVF3708g, the response rate was 25.9% (95% CI: 17%, 36.1%) with a median duration of response of 4.2 months (95% CI: 3, 5.7). In Study NCI 06-C-0064E, the response rate was 19.6% (95% CI: 10.9%, 31.3%) with a median duration of response of 3.9 months (95% CI: 2.4, 17.4).

14.5 Metastatic Renal Cell Carcinoma

Study BO17705

The safety and efficacy of Avastin were evaluated in patients with treatment-naïve mRCC in a multicenter, randomized, double-blind, international study [BO17705 (NCT00738530)] comparing interferon alfa and Avastin versus interferon alfa and placebo. A total of 649 patients who had undergone a nephrectomy were randomized (1:1) to receive either Avastin (10 mg/kg every 2 weeks; N = 327) or placebo (every 2 weeks; N = 322) with interferon alfa (9 MIU subcutaneously three times weekly for a maximum of 52 weeks). Patients were treated until disease progression or unacceptable toxicity. The main outcome measure was investigator-assessed PFS. Secondary outcome measures were ORR and OS.

The median age was 60 years (18 to 82 years); 70% were male and 96% were White. The study population was characterized by Motzer scores as follows: 28% favorable (0), 56% intermediate (1-2), 8% poor (3–5), and 7% missing.

PFS was statistically significantly prolonged among patients receiving Avastin compared to placebo; median PFS was 10.2 months vs. 5.4 months [HR 0.60 (95% CI: 0.49, 0.72), p-value < 0.0001, stratified log-rank test]. Among the 595 patients with measurable disease, ORR was also significantly higher (30% vs. 12%, p-value < 0.0001, stratified CMH test). There was no improvement in OS based on the final analysis conducted after 444 deaths, with a median OS of 23 months in the patients receiving Avastin with interferon alfa and 21 months in patients receiving interferon alone [HR 0.86, (95% CI: 0.72, 1.04)]. Results are presented in Figure 4.

Figure 4: Kaplan-Meier Curves for Progression-Free Survival in Metastatic Renal Cell Carcinoma in Study BO17705

14.6 Persistent, Recurrent, or Metastatic Cervical Cancer

Study GOG-0240

The safety and efficacy of Avastin were evaluated in patients with persistent, recurrent, or metastatic cervical cancer in a randomized, four-arm, multicenter study comparing Avastin with chemotherapy versus chemotherapy alone [GOG-0240 (NCT00803062)]. A total of 452 patients were randomized (1:1:1:1) to receive paclitaxel and cisplatin with or without Avastin, or paclitaxel and topotecan with or without Avastin.

The dosing regimens for Avastin, paclitaxel, cisplatin and topotecan were as follows:

- Day 1: Paclitaxel 135 mg/m^2 over 24 hours, Day 2: cisplatin 50 mg/m^2 with Avastin;
- Day 1: Paclitaxel 175 mg/m^2 over 3 hours, Day 2: cisplatin 50 mg/m^2 with Avastin;
- Day 1: Paclitaxel 175 mg/m^2 over 3 hours with cisplatin 50 mg/m^2 with Avastin;
- Day 1: Paclitaxel 175 mg/m^2 over 3 hours with Avastin, Days 1-3: topotecan IV 0.75 mg/m^2 over 30 minutes

Patients were treated until disease progression or unacceptable adverse reactions. The main outcome measure was OS. Secondary outcome measures included ORR.

The median age was 48 years (20 to 85 years). Of the 452 patients randomized at baseline, 78% of patients were White, 80% had received prior radiation, 74% had received prior chemotherapy concurrent with radiation, and 32% had a platinum-free interval (PFI) of less than 6 months. Patients had a GOG performance status of 0 (58%) or 1 (42%). Demographic and disease characteristics were balanced across arms.

Results are presented in Figure 5 and Table 13.

Figure 5: Kaplan-Meier Curves for Overall Survival in Persistent, Recurrent, or Metastatic Cervical Cancer in Study GOG-0240

Table 13: Efficacy Results in Study GOG-0240
Efficacy Parameter | Avastin with Chemotherapy (N=227) | Chemotherapy (N=225)
Overall Survival
Median, in months [Kaplan-Meier estimates.] | 16.8 | 12.9
Hazard ratio (95% CI) | 0.74 (0.58, 0.94)
p-value [log-rank test (stratified).] | 0.0132

The ORR was higher in patients who received Avastin with chemotherapy [45% (95% CI: 39, 52)] compared to patients who received chemotherapy alone [34% (95% CI: 28,40)].

Table 14: Efficacy Results in Study GOG-0240
Efficacy Parameter | Topotecan and Paclitaxel with or without Avastin (N=223) | Cisplatin and Paclitaxel with or without Avastin (N=229)
Overall Survival
Median, in months [Kaplan-Meier estimates.] | 13.3 | 15.5
Hazard ratio (95% CI) | 1.15 (0.91, 1.46)
p-value | 0.23

The HR for OS with Avastin with cisplatin and paclitaxel as compared to cisplatin and paclitaxel alone was 0.72 (95% CI: 0.51,1.02). The HR for OS with Avastin with topotecan and paclitaxel as compared to topotecan and paclitaxel alone was 0.76 (95% CI: 0.55, 1.06).

14.7 Stage III or IV Epithelial Ovarian, Fallopian Tube, or Primary Peritoneal Cancer Following Initial Surgical Resection

Study GOG-0218

The safety and efficacy of Avastin were evaluated in a multicenter, randomized, double-blind, placebo controlled, three arm study [Study GOG-0218 (NCT00262847)] evaluating the effect of adding Avastin to carboplatin and paclitaxel for the treatment of patients with stage III or IV epithelial ovarian, fallopian tube or primary peritoneal cancer (N=1873) following initial surgical resection. Patients were randomized (1:1:1) to one of the following arms:

- CPP: carboplatin (AUC 6) and paclitaxel (175 mg/m^2) for six cycles, with concurrent placebo started at cycle 2, followed by placebo alone every three weeks for a total of up to 22 cycles of therapy (n=625) or
- CPB15: carboplatin (AUC 6) and paclitaxel (175 mg/m^2) for six cycles, with concurrent Avastin started at cycle 2, followed by placebo alone every three weeks for a total of up to 22 cycles of therapy (n=625) or
- CPB15+: carboplatin (AUC 6) and paclitaxel (175 mg/m^2) for six cycles, with concurrent Avastin started at cycle 2, followed by Avastin as a single agent every three weeks for a total of up to 22 cycles of therapy (n=623).

The main outcome measure was investigator-assessed PFS. OS was a secondary outcome measure.

The median age was 60 years (range 22-89 years) and 28% of patients were >65 years of age.

Overall, approximately 50% of patients had a GOG PS of 0 at baseline, and 43% a GOG PS score of 1. Patients had either epithelial ovarian cancer (83%), primary peritoneal cancer (15%), or fallopian tube cancer (2%). Serous adenocarcinoma was the most common histologic type (85% in CPP and CPB15 arms, 86% in CPB15+ arm). Overall, approximately 34% of patients had resected FIGO Stage III with residual disease < 1 cm, 40% had resected Stage III with residual disease >1 cm, and 26% had resected Stage IV disease.

The majority of patients in all three treatment arms received subsequent antineoplastic treatment, 78.1% in the CPP arm, 78.6% in the CPB15 arm, and 73.2% in the CPB15+ arm. A higher proportion of patients in the CPP arm (25.3%) and CPB15 arm (26.6%) received at least one anti-angiogenic (including bevacizumab) treatment after discontinuing from study compared with the CPB15+ arm (15.6%).

Study results are presented in Table 15 and Figure 6.

Table 15: Efficacy Results in Study GOG-0218
Efficacy Parameter | Avastin with carboplatin and paclitaxel followed by Avastin alone (N=623) | Avastin with carboplatin and paclitaxel (N=625) | Carboplatin and paclitaxel (N= 625)
Progression-Free Survival per Investigator
Median, in months | 18.2 | 12.8 | 12.0
Hazard ratio (95% CI) [Relative to the control arm; stratified hazard ratio] | 0.62 (0.52, 0.75) | 0.83 (0.70, 0.98)
p –value [Two-sided p-value based on re-randomization test] | < 0.0001 | NS
Overall Survival [Final overall survival analysis]
Median, in months | 43.8 | 38.8 | 40.6
Hazard ratio (95% CI) | 0.89 (0.76, 1.05) | 1.06 (0.90, 1.24)
NS=not significant

Figure 6: Kaplan-Meier Curves for Investigator-Assessed Progression-Free Survival in Stage III or IV Epithelial Ovarian, Fallopian Tube, or Primary Peritoneal Cancer Following Initial Surgical Resection in Study GOG-0218

14.8 Platinum-Resistant Recurrent Epithelial Ovarian, Fallopian Tube, or Primary Peritoneal Cancer

Study MO22224

The safety and efficacy of Avastin were evaluated in a multicenter, open-label, randomized study [MO22224 (NCT00976911)] comparing Avastin with chemotherapy versus chemotherapy alone in patients with platinum-resistant, recurrent epithelial ovarian, fallopian tube, or primary peritoneal cancer that recurred within <6 months from the most recent platinum-based therapy (N=361). Patients had received no more than 2 prior chemotherapy regimens. Patients received one of the following chemotherapy regimens at the discretion of the investigator: paclitaxel (80 mg/m^2 on days 1, 8, 15 and 22 every 4 weeks; pegylated liposomal doxorubicin 40 mg/m^2 on day 1 every 4 weeks; or topotecan 4 mg/m^2 on days 1, 8 and 15 every 4 weeks or 1.25 mg/m^2 on days 1-5 every 3 weeks). Patients were treated until disease progression, unacceptable toxicity, or withdrawal. Forty percent of patients on the chemotherapy alone arm received Avastin alone upon progression. The main outcome measure was investigator-assessed PFS. Secondary outcome measures were ORR and OS.

The median age was 61 years (25 to 84 years) and 37% of patients were ≥65 years. Seventy-nine percent had measurable disease at baseline, 87% had baseline CA-125 levels ≥2 times ULN and 31% had ascites at baseline. Seventy-three percent had a PFI of 3 months to 6 months and 27% had PFI of <3 months. ECOG performance status was 0 for 59%, 1 for 34% and 2 for 7% of the patients.

The addition of Avastin to chemotherapy demonstrated a statistically significant improvement in investigator-assessed PFS, which was supported by a retrospective independent review analysis. Results for the ITT population are presented in Table 16 and Figure 7. Results for the separate chemotherapy cohorts are presented in Table 17.

Table 16: Efficacy Results in Study MO22224
Efficacy Parameter | Avastin with Chemotherapy (N=179) | Chemotherapy (N=182)
Progression-Free Survival per Investigator
Median (95% CI), in months | 6.8 (5.6, 7.8) | 3.4 (2.1, 3.8)
HR (95% CI) [per stratified Cox proportional hazards model] | 0.38 (0.30, 0.49)
p-value [per stratified log-rank test] | <0.0001
Overall Survival
Median (95% CI), in months | 16.6 (13.7, 19.0) | 13.3 (11.9, 16.4)
HR (95% CI) | 0.89 (0.69, 1.14)
Overall Response Rate
Number of Patients with Measurable Disease at Baseline | 142 | 144
Rate, % (95% CI) | 28% (21%, 36%) | 13% (7%, 18%)
Duration of Response
Median, in months | 9.4 | 5.4

Figure 7: Kaplan-Meier Curves for Investigator-Assessed Progression-Free Survival in Platinum-Resistant Recurrent Epithelial Ovarian, Fallopian Tube, or Primary Peritoneal Cancer in Study MO22224

Table 17: Efficacy Results in Study MO22224 by Chemotherapy
Efficacy Parameter | Paclitaxel |  | Topotecan |  | Pegylated Liposomal Doxorubicin
Efficacy Parameter | Avastin with Chemotherapy | Chemotherapy | Avastin with Chemotherapy | Chemotherapy | Avastin with Chemotherapy | Chemotherapy
Efficacy Parameter | (N=60) | (N=55) | (N=57) | (N=63) | (N=62) | (N=64)
Progression-Free Survival per Investigator
Median, in months (95% CI) | 9.6 (7.8, 11.5) | 3.9 (3.5, 5.5) | 6.2 (5.3, 7.6) | 2.1 (1.9, 2.3) | 5.1 (3.9, 6.3) | 3.5 (1.9, 3.9)
Hazard ratio [per stratified Cox proportional hazards model] (95% CI) | 0.47 (0.31, 0.72) |  | 0.24 (0.15, 0.38) |  | 0.47 (0.32, 0.71)
Overall Survival
Median, in months (95% CI) | 22.4 (16.7, 26.7) | 13.2 (8.2, 19.7) | 13.8 (11.0, 18.3) | 13.3 (10.4, 18.3) | 13.7 (11.0, 18.3) | 14.1 (9.9, 17.8)
Hazard ratio (95% CI) | 0.64 (0.41, 1.01) |  | 1.12 (0.73, 1.73) |  | 0.94 (0.63, 1.42)
Overall Response Rate
Number of patients with measurable disease at baseline | 45 | 43 | 46 | 50 | 51 | 51
Rate, % (95% CI) | 53 (39, 68) | 30 (17, 44) | 17 (6, 28) | 2 (0, 6) | 16 (6, 26) | 8 (0, 15)
Duration of Response
Median, in months | 11.6 | 6.8 | 5.2 | NE | 8.0 | 4.6
NE=Not Estimable

14.9 Platinum-Sensitive Recurrent Epithelial Ovarian, Fallopian Tube, or Primary Peritoneal Cancer

Study AVF4095g

The safety and efficacy of Avastin were evaluated in a randomized, double-blind, placebo-controlled study [AVF4095g (NCT00434642)] studying Avastin with chemotherapy versus chemotherapy alone in the treatment of patients with platinum-sensitive recurrent epithelial ovarian, fallopian tube, or primary peritoneal cancer who have not received prior chemotherapy in the recurrent setting or prior bevacizumab treatment (N=484). Patients were randomized (1:1) to receive Avastin (15 mg/kg day 1) or placebo every 3 weeks with carboplatin (AUC 4, day 1) and gemcitabine (1000 mg/m^2 on days 1 and 8) a for 6 to 10 cycles followed by Avastin or placebo alone until disease progression or unacceptable toxicity. The main outcome measures were investigator-assessed PFS. Secondary outcome measures were ORR and OS.

The median age was 61 years (28 to 87 years) and 37% of patients were ≥65 years. All patients had measurable disease at baseline, 74% had baseline CA-125 levels >ULN (35 U/mL). The platinum-free interval (PFI) was 6 months to 12 months in 42 % of patients and >12 months in 58% of patients. The ECOG performance status was 0 or 1 for 99.8% of patients.

A statistically significant prolongation in PFS was demonstrated among patients receiving Avastin with chemotherapy compared to those receiving placebo with chemotherapy (Table 18 and Figure 8). Independent radiology review of PFS was consistent with investigator assessment [HR 0.45 (95% CI: 0.35, 0.58)]. OS was not significantly improved with the addition of Avastin to chemotherapy [HR 0.95 (95% CI: 0.77, 1.17)].

Table 18: Efficacy Results in Study AVF4095g
Efficacy Parameter | Avastin with Gemcitabine and Carboplatin (N=242) | Placebo with Gemcitabine and Carboplatin (N=242)
Progression-Free Survival
Median, in months | 12.4 | 8.4
Hazard ratio (95% CI) | 0.46 (0.37, 0.58)
p-value | < 0.0001
Overall Response Rate
% patients with overall response | 78% | 57%
p-value | < 0.0001

Figure 8: Kaplan-Meier Curves for Progression-Free Survival in Platinum-Sensitive Recurrent Epithelial Ovarian, Fallopian Tube, or Primary Peritoneal Cancer in Study AVF4095g

Study GOG-0213

The safety and efficacy of Avastin were evaluated in a randomized, controlled, open-label study [Study GOG-0213 (NCT00565851)] of Avastin with chemotherapy versus chemotherapy alone in the treatment of patients with platinum-sensitive recurrent epithelial ovarian, fallopian tube, or primary peritoneal cancer, who have not received more than one previous regimen of chemotherapy (N=673). Patients were randomized (1:1) to receive carboplatin (AUC 5) and paclitaxel (175 mg/m^2 IV over 3 hours) every 3 weeks for 6 to 8 cycles (N=336) or Avastin (15 mg/kg) every 3 weeks with carboplatin (AUC 5) and paclitaxel (175 mg/m^2 IV over 3 hours) for 6 to 8 cycles followed by Avastin (15 mg/kg every 3 weeks) as a single agent until disease progression or unacceptable toxicity. The main outcome measure was OS. Other outcome measures were investigator-assessed PFS, and ORR.

The median age was 60 years (23 to 85 years) and 33% of patients were ≥ 65 years. Eighty-three percent had measurable disease at baseline and 74% had abnormal CA-125 levels at baseline. Ten percent of patients had received prior bevacizumab. Twenty-six percent had a PFI of 6 months to 12 months and 74% had a PFI of >12 months. GOG performance status was 0 or 1 for 99% of patients.

Results are presented in Table 19 and Figure 9.

Table 19: Efficacy Results in Study GOG-0213
Efficacy Parameter | Avastin with Carboplatin and Paclitaxel (N=337) | Carboplatin and Paclitaxel (N=336)
Overall Survival
Median, in months | 42.6 | 37.3
Hazard ratio (95% CI) (IVRS) [HR was estimated from Cox proportional hazards models stratified by the duration of treatment free-interval prior to enrolling onto this study per IVRS (interactive voice response system) and secondary surgical debulking status.] | 0.84 (0.69, 1.01)
Hazard ratio (95% CI) (eCRF) [HR was estimated from Cox proportional hazards models stratified by the duration of platinum free-interval prior to enrolling onto this study per eCRF (electronic case report form) and secondary surgical debulking status.] | 0.82 (0.68, 0.996)
Progression-Free Survival
Median, in months | 13.8 | 10.4
Hazard ratio (95% CI) (IVRS) | 0.61 (0.51, 0.72)
Overall Response Rate
Number of patients with measurable disease at baseline | 274 | 286
Rate, % | 213 (78%) | 159 (56%)

Figure 9: Kaplan Meier Curves for Overall Survival in Platinum-Sensitive Recurrent Epithelial Ovarian, Fallopian Tube, or Primary Peritoneal Cancer in Study GOG-0213

14.10 Hepatocellular Carcinoma

The efficacy of Avastin in combination with atezolizumab was investigated in IMbrave150 (NCT03434379), a multicenter, international, open-label, randomized trial in patients with locally advanced unresectable and/or metastatic hepatocellular carcinoma who have not received prior systemic therapy. Randomization was stratified by geographic region (Asia excluding Japan vs. rest of world), macrovascular invasion and/or extrahepatic spread (presence vs. absence), baseline AFP (<400 vs. ≥400 ng/mL), and by ECOG performance status (0 vs. 1).

A total of 501 patients were randomized (2:1) to receive either atezolizumab as an intravenous infusion of 1200 mg, followed by 15 mg/kg Avastin, on the same day every 3 weeks or sorafenib 400 mg given orally twice daily, until disease progression or unacceptable toxicity. Patients could discontinue either atezolizumab or Avastin (e.g., due to adverse events) and continue on single-agent therapy until disease progression or unacceptable toxicity associated with the single-agent.

The study enrolled patients who were ECOG performance score 0 or 1 and who had not received prior systemic treatment. Patients were required to be evaluated for the presence of varices within 6 months prior to treatment, and were excluded if they had variceal bleeding within 6 months prior to treatment, untreated or incompletely treated varices with bleeding, or high risk of bleeding. Patients with Child-Pugh B or C cirrhosis, moderate or severe ascites; history of hepatic encephalopathy; a history of autoimmune disease; administration of a live, attenuated vaccine within 4 weeks prior to randomization; administration of systemic immunostimulatory agents within 4 weeks or systemic immunosuppressive medications within 2 weeks prior to randomization; or untreated or corticosteroid-dependent brain metastases were excluded. Tumor assessments were performed every 6 weeks for the first 54 weeks and every 9 weeks thereafter.

The demographics and baseline disease characteristics of the study population were balanced between the treatment arms. The median age was 65 years (range: 26 to 88) and 83% of patients were male. The majority of patients were Asian (57%) or White (35%); 40% were from Asia (excluding Japan). Approximately 75% of patients presented with macrovascular invasion and/or extrahepatic spread and 37% had a baseline AFP ≥400 ng/mL. Baseline ECOG performance status was 0 (62%) or 1 (38%). HCC risk factors were Hepatitis B in 48% of patients, Hepatitis C in 22% and 31% of patients had non-viral liver disease. The majority of patients had BCLC stage C (82%) disease at baseline, while 16% had stage B and 3% had stage A.

The major efficacy outcome measures were overall survival (OS) and independent review facility (IRF)-assessed progression free survival (PFS) per RECIST v1.1. Additional efficacy outcome measures were IRF-assessed overall response rate (ORR) per RECIST and mRECIST.

Efficacy results are presented in Table 20 and Figure 10.

Table 20: Efficacy Results from IMbrave150
 | Avastin in combination with Atezolizumab (N= 336) | Sorafenib (N=165)
 | Overall Survival
Number of deaths (%) | 96 (29) | 65 (39)
Median OS in months (95% CI) | NE (NE, NE) | 13.2 (10.4, NE)
Hazard ratio [Stratified by geographic region (Asia excluding Japan vs. rest of world), macrovascular invasion and/or extrahepatic spread (presence vs. absence), and baseline AFP (<400 vs. ≥400 ng/mL)] (95% CI) | 0.58 (0.42, 0.79)
p-value [Based on two-sided stratified log-rank test; as compared to significance level 0.004 (2-sided) based on 161/312=52% information using the OBF method] | 0.0006
 | Progression-Free Survival [Per independent radiology review]
Number of events(%) | 197 (59) | 109 (66)
Median PFS in months (95% CI) | 6.8 (5.8, 8.3) | 4.3 (4.0, 5.6)
Hazard ratio (95% CI) | 0.59 (0.47, 0.76)
p-value | <0.0001
 | Overall Response Rate, [Confirmed responses] (ORR), RECIST 1.1
Number of responders (%) | 93 (28) | 19 (12)
(95% CI) | (23, 33) | (7,17)
p-value [Based on two-sided Cochran-Mantel-Haesnszel test] | <0.0001
Complete responses, n (%) | 22 (7) | 0
Partial responses, n (%) | 71 (21) | 19 (12)
 | Duration of Response, (DOR) RECIST 1.1
 | (n=93) | (n=19)
Median DOR in months (95% CI) | NE (NE, NE) | 6.3 (4.7, NE)
Range (months) | (1.3 [Denotes a censored value] , 13.4) | (1.4, 9.1)
 | Overall Response Rate, (ORR), HCC mRECIST
Number of responders (%) | 112 (33) | 21 (13)
(95% CI) | (28, 39) | (8, 19)
p-value | <0.0001
Complete responses, n (%) | 37 (11) | 3 (1.8)
Partial responses, n (%) | 75 (22) | 18 (11)
 | Duration of Response, (DOR) HCC mRECIST
 | (n=112) | (n=21)
Median DOR in months (95% CI) | NE (NE, NE) | 6.3 (4.9, NE)
Range (months) | (1.3, 13.4) | (1.4, 9.1)
CI=confidence interval; HCC mRECIST= Modified RECIST Assessment for Hepatocellular Carcinoma; NE=not estimable; N/A=not applicable; RECIST 1.1= Response Evaluation Criteria in Solid Tumors v1.1

Figure 10: Kaplan-Meier Plot of Overall Survival in IMbrave150

16 HOW SUPPLIED/STORAGE AND HANDLING

Avastin (bevacizumab) injection is a clear to slightly opalescent, colorless to pale brown, sterile solution for intravenous infusion supplied as single-dose vials in the following strengths:

- 100 mg/4 mL (25 mg/mL): carton of one vial (NDC 50242-060-01)
- 400 mg/16 mL (25 mg/mL): carton of one vial (NDC 50242-061-01)

STORAGE AND HANDLING

Store refrigerated at 2°C to 8°C (36°F to 46°F) in the original carton until time of use to protect from light. Do not freeze or shake the vial or carton.

17 PATIENT COUNSELING INFORMATION

Gastrointestinal Perforations and Fistulae: Avastin may increase the risk of developing gastrointestinal perforations and fistulae. Advise patients to immediately contact their healthcare provider for high fever, rigors, persistent or severe abdominal pain, severe constipation, or vomiting [see Warnings and Precautions (5.1)].

Surgery and Wound Healing Complications: Avastin can increase the risk of wound healing complications. Instruct patients not to undergo surgery without first discussing this potential risk with their healthcare provider [see Warnings and Precautions (5.2)].

Hemorrhage: Avastin can increase the risk of hemorrhage. Advise patients to immediately contact their healthcare provider for signs and symptoms of serious or unusual bleeding including coughing or spitting blood [see Warnings and Precautions (5.3)].

Arterial and Venous Thromboembolic Events: Avastin increases the risk of arterial and venous thromboembolic events. Advise patients to immediately contact their healthcare provider for signs and symptoms of arterial or venous thromboembolism [see Warnings and Precautions (5.4, 5.5)].

Hypertension: Avastin can increase blood pressure. Advise patients that they will undergo routine blood pressure monitoring and to contact their healthcare provider if they experience changes in blood pressure [see Warnings and Precautions (5.6)].

Posterior Reversible Leukoencephalopathy Syndrome: Posterior reversible encephalopathy syndrome (PRES) has been associated with Avastin treatment. Advise patients to immediately contact their healthcare provider for new onset or worsening neurological function [see Warnings and Precautions (5.7)].

Renal Injury and Proteinuria: Avastin increases the risk of proteinuria and renal injury, including nephrotic syndrome. Advise patients that treatment with Avastin requires regular monitoring of renal function and to contact their healthcare provider for proteinuria or signs and symptoms of nephrotic syndrome [see Warnings and Precautions (5.8)].

Infusion-Related Reactions: Avastin can cause infusion-related reactions. Advise patients to contact their healthcare provider immediately for signs or symptoms of infusion-related reactions [see Warnings and Precautions (5.9)].

Congestive Heart Failure: Avastin can increase the risk of developing congestive heart failure. Advise patients to contact their healthcare provider immediately for signs and symptoms of CHF [see Warnings and Precautions (5.12)].

Embryo-Fetal Toxicity: Advise female patients that Avastin may cause fetal harm and to inform their healthcare provider with a known or suspected pregnancy [see Warnings and Precautions (5.10), Use in Specific Populations (8.1)]. Advise females of reproductive potential to use effective contraception during treatment with Avastin and for 6 months after the last dose [see Use in Specific Populations (8.3)].

Ovarian Failure: Avastin may lead to ovarian failure. Advise patients of potential options for preservation of ova prior to starting treatment [see Warnings and Precautions (5.11)].

Lactation: Advise women not to breastfeed during treatment with Avastin and for 6 months after the last dose [see Use in Specific Populations (8.2)].

Avastin® (bevacizumab)
Manufactured by:
Genentech, Inc.
A Member of the Roche Group
1 DNA Way
South San Francisco, CA 94080-4990
U.S. License No.: 1048

Avastin® is a registered trademark of Genentech, Inc.
©2022 Genentech, Inc.

Representative sample of labeling (see the HOW SUPPLIED section for complete listing):

PRINCIPAL DISPLAY PANEL - 4 mL Vial Carton

NDC 50242-060-01

100 mg/4 mL
(25 mg/mL)

AVASTIN®
(bevacizumab)
Injection

For Intravenous Use.

Single-Dose Vial.
Discard Unused Portion.
No preservative.

1 vial
Rx only

Genentech

10213744

PRINCIPAL DISPLAY PANEL - 16 mL Vial Carton

NDC 50242-061-01

400 mg/16 mL
(25 mg/mL)

AVASTIN®
(bevacizumab)
Injection

For Intravenous Use.

Single-Dose Vial.
Discard Unused Portion.
No preservative.

1 vial
Rx only

10213746